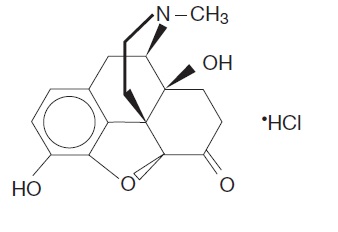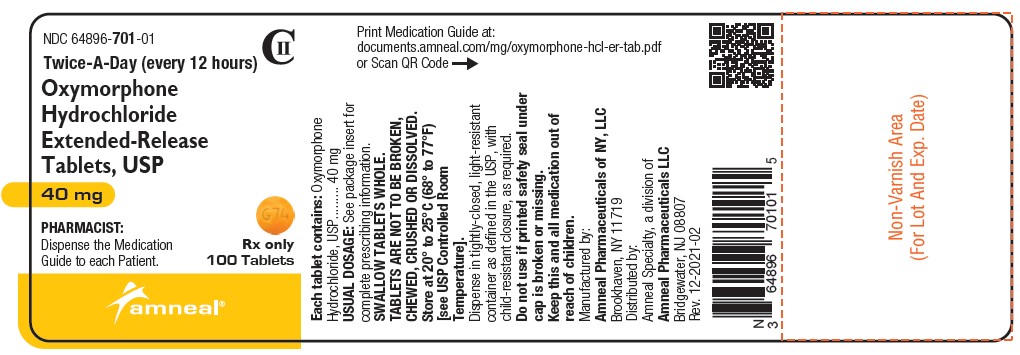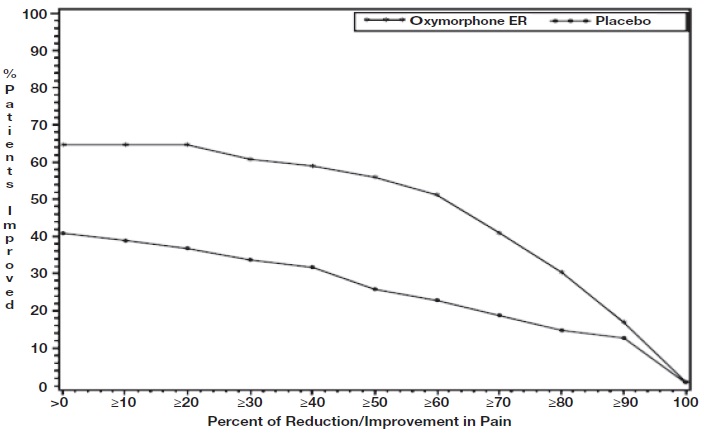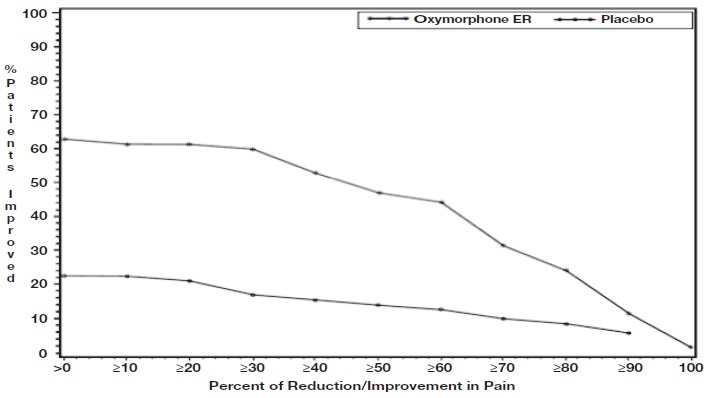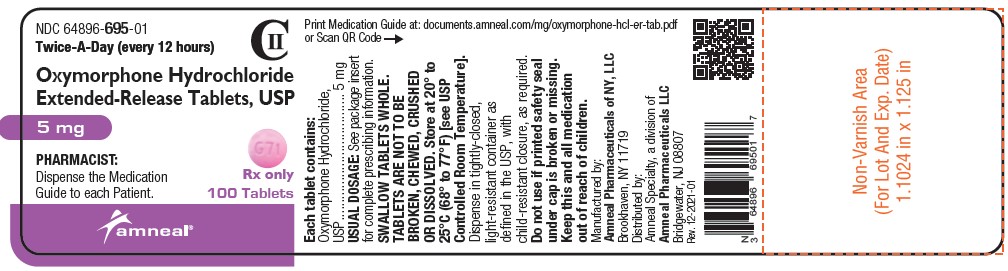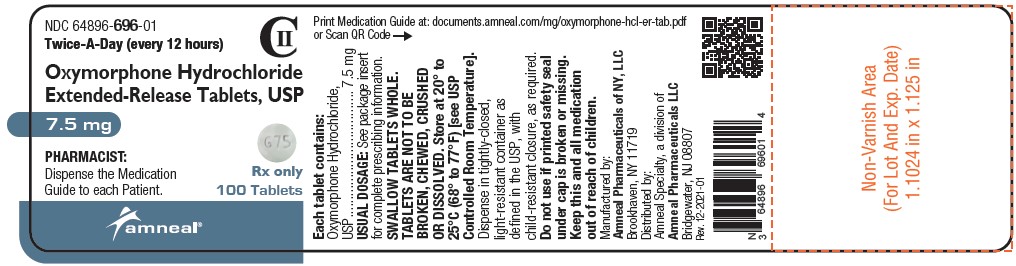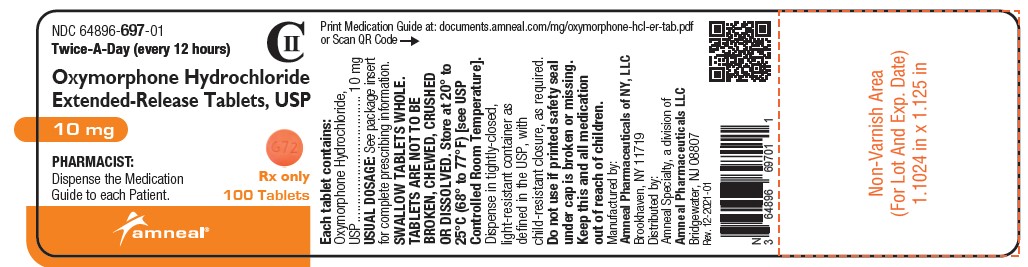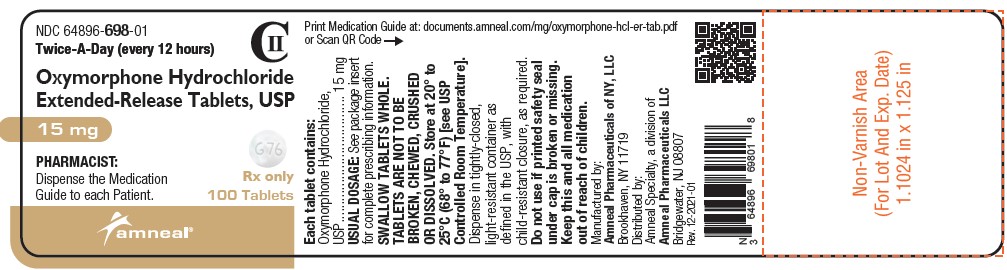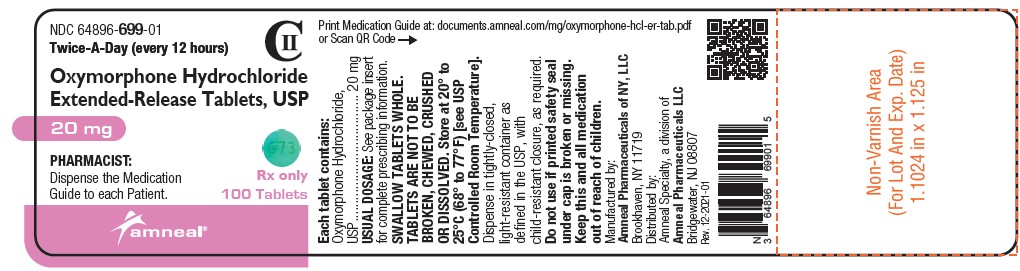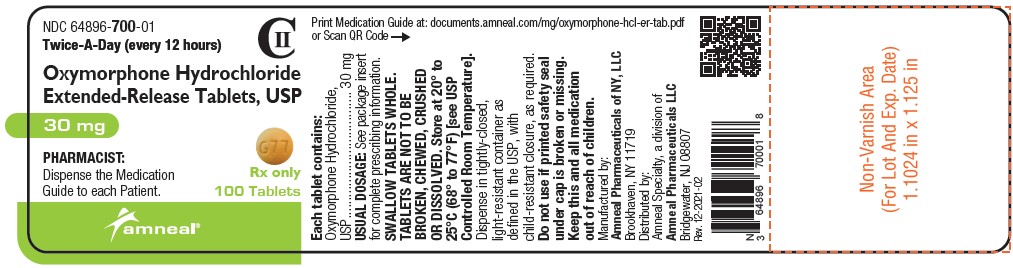 DRUG LABEL: Oxymorphone hydrochloride
NDC: 64896-695 | Form: TABLET, FILM COATED, EXTENDED RELEASE
Manufacturer: Amneal Pharmaceuticals LLC
Category: prescription | Type: HUMAN PRESCRIPTION DRUG LABEL
Date: 20260115
DEA Schedule: CII

ACTIVE INGREDIENTS: OXYMORPHONE HYDROCHLORIDE 5 mg/1 1
INACTIVE INGREDIENTS: CELLULOSE, MICROCRYSTALLINE; LACTOSE MONOHYDRATE; HYPROMELLOSES; XANTHAN GUM; MAGNESIUM STEARATE; POLYVINYL ALCOHOL, UNSPECIFIED; POLYETHYLENE GLYCOL, UNSPECIFIED; TALC; TITANIUM DIOXIDE; FD&C YELLOW NO. 6; ALUMINUM OXIDE; FD&C BLUE NO. 2; D&C RED NO. 27

HIGHLIGHTS OF PRESCRIBING INFORMATION

These highlights do not include all the information needed to use OXYMORPHONE HYDROCHLORIDE EXTENDED-RELEASE TABLETS safely and effectively. See full prescribing information for OXYMORPHONE HYDROCHLORIDE EXTENDED-RELEASE TABLETS.
OXYMORPHONE HYDROCHLORIDE extended-release tablets, for oral use, CII
Initial U.S. Approval: 1959

WARNING: SERIOUS AND LIFE-THREATENING RISKS FROM USE OF OXYMORPHONE HYDROCHLORIDE EXTENDED-RELEASE TABLETS

See full prescribing information for complete boxed warning.

- Oxymorphone Hydrochloride Extended-Release Tablets expose users to risks of addiction, abuse, and misuse, which can lead to overdose and death. Assess patient’s risk before prescribing and reassess regularly these behaviors and conditions. (5.1)
- Serious life-threatening or fatal respiratory depression may occur, especially during initiation or following a dosage increase. To reduce the risk of respiratory depression, proper dosing and titration of Oxymorphone Hydrochloride Extended-Release Tablets are essential. Instruct patients to swallow Oxymorphone Hydrochloride Extended-Release Tablets whole to avoid exposure to a potentially fatal dose of oxymorphone. (2.1, 5.2)
- Accidental ingestion of Oxymorphone Hydrochloride Extended-Release Tablets, especially by children, can result in fatal overdose of oxymorphone. (5.2)
- Instruct patients not to consume alcohol or any product containing alcohol while taking Oxymorphone Hydrochloride Extended-Release Tablets because co-ingestion can result in fatal plasma oxymorphone levels. (5.3)
- Concomitant use of opioids with benzodiazepines or other central nervous system (CNS) depressants, including alcohol, may result in profound sedation, respiratory depression, coma, and death. Reserve concomitant prescribing for use in patients for whom alternative treatment options are inadequate. (5.3, 7)
- Advise pregnant women using opioids for an extended period of time of the risk of Neonatal Opioid Withdrawal Syndrome, which may be life-threatening if not recognized and treated. Ensure that management by neonatology experts will be available at delivery. (5.4)
- Healthcare providers are strongly encouraged to complete a REMS compliant education program and to counsel patients and caregivers on serious risks, safe use and the importance of reading the Medication Guide with each prescription. (5.5)

RECENT MAJOR CHANGES

Boxed Warning

Indications and Usage (1) 08/2025

Dosage and Administration (2.2, 2.3, 2.5) 08/2025

Warnings and Precautions (5.1, 5.2, 5.3, 5.13, 5.15) 08/2025

1 INDICATIONS AND USAGE

Oxymorphone Hydrochloride Extended-Release Tablets are an opioid agonist indicated for the management of severe and persistent pain that requires an opioid analgesic and that cannot be adequately treated with alternative options, including immediate-release opioids. (1)

Limitations of Use (1)

- Because of the risks of addiction, abuse, misuse, overdose and death, which can occur at any dosage or duration and persist over the course of therapy, reserve opioid analgesics, including Oxymorphone Hydrochloride Extended-Release Tablets for use in patients for whom alternative treatment options are ineffective, not tolerated, or would be otherwise inadequate to provide sufficient management of pain. (1, 5.1)
- Oxymorphone Hydrochloride Extended-Release Tablets are not indicated as an as-needed (prn) analgesic. (1)

2 DOSAGE AND ADMINISTRATION

- Oxymorphone Hydrochloride Extended-Release Tablets should be prescribed only by healthcare professionals who are knowledgeable about the use of extended-release/long-acting opioids and how to mitigate the associated risks. (2.1)
- Use the lowest effective dosage for the shortest duration of time consistent with individual patient treatment goals. Reserve titration to higher doses of Oxymorphone Hydrochloride Extended-Release Tablets for patients in whom lower doses are insufficiently effective and in whom the expected benefits of using a higher dose opioid clearly outweigh the substantial risks. (2.1, 5)
- Initiate the dosing regimen for each patient individually, taking into account the patient’s underlying cause and severity of pain, prior analgesic treatment and response, and risk factors for addiction, abuse, and misuse. (2.1, 5.1)
- Respiratory depression can occur at any time during opioid therapy, especially when initiating and following dosage increases with Oxymorphone Hydrochloride Extended-Release Tablets. Consider this risk when selecting an initial dose and when making dose adjustments. (2.1, 5.1)
- Discuss opioid overdose reversal agents and options for acquiring them with the patient and/or caregiver, both when initiating and renewing treatment with Oxymorphone Hydrochloride Extended-Release Tablets, especially if the patient has additional risk factors for overdose, or close contacts at risk for exposure and overdose. (2.2, 5.1, 5.2, 5.3).
- Oxymorphone Hydrochloride Extended-Release Tablets are administered orally twice daily (every 12 hours), on an empty stomach, at least 1 hour prior to or 2 hours after eating. (2.1, 2.3)
- For patients who are not opioid tolerant, initiate treatment with 5 mg tablets orally every 12 hours. (2.3)
- To convert to Oxymorphone Hydrochloride Extended-Release Tablets from another opioid, use available conversion factors to obtain estimated dose. (2.3)
- Dose can be increased every 3 to 7 days, using increments of 5 mg to 10 mg every 12 hours (i.e., 10 mg to 20 mg per day). (2.4)
- Periodically reassess patients receiving Oxymorphone Hydrochloride Extended-Release Tablets to evaluate the continued need for opioid analgesics to maintain pain control, for the signs or symptoms of adverse reactions, and for the development of addiction, abuse, or misuse. (2.4)
- Mild Hepatic Impairment: For patients who are not opioid tolerant, initiate treatment with 5 mg and titrate slowly. For patients on prior opioid therapy, reduce starting dose by 50% and titrate slowly. Evaluate for signs of respiratory and central nervous system depression. (2.6)
- Renal Impairment: For patients who are not opioid tolerant, initiate treatment with 5 mg and titrate slowly. For patients on prior opioid therapy, reduce starting dose by 50% and titrate slowly. Evaluate for signs of respiratory and central nervous system depression. (2.7)
- Geriatric Patients: Initiate dosing with 5 mg, titrate slowly, and evaluate for signs of respiratory and central nervous system depression. (2.8)
- Do not rapidly reduce or abruptly discontinue Oxymorphone Hydrochloride Extended-Release Tablets in a physically dependent patient because rapid reduction or abrupt discontinuation of opioid analgesics has resulted in serious withdrawal symptoms, uncontrolled pain, and suicide. (2.5, 5.15)

3 DOSAGE FORMS AND STRENGTHS

Extended-release tablets: 5 mg, 7.5 mg, 10 mg, 15 mg, 20 mg, 30 mg, and 40 mg

4 CONTRAINDICATIONS

- Significant respiratory depression (4)
- Acute or severe bronchial asthma in an unmonitored setting or in absence of resuscitative equipment (4)
- Hypersensitivity to oxymorphone (4)
- Moderate or severe hepatic impairment (4)
- Known or suspected gastrointestinal obstruction, including paralytic ileus (4)

5 WARNINGS AND PRECAUTIONS

- Opioid-Induced Hyperalgesia and Allodynia: Opioid-Induced Hyperalgesia (OIH) occurs when an opioid analgesic paradoxically causes an increase in pain, or an increase in sensitivity to pain. If OIH is suspected, carefully consider appropriately decreasing the dose of the current opioid analgesic, or opioid rotation. (5.6)
- Life-Threatening Respiratory Depression in Patients with Chronic Pulmonary Disease or in Elderly Cachectic or Debilitated Patients: Regularly evaluate particularly during initiation and titration. (5.7)
- Anaphylaxis, Angioedema, and Other Hypersensitivity Reactions: If symptoms occur, stop administration immediately, discontinue permanently, and do not rechallenge with any other oxymorphone formulation. (5.8)
- Adrenal Insufficiency: If diagnosed, treat with physiologic replacement of corticosteroids, and wean patient off of the opioid. (5.9)
- Severe Hypotension: Regularly evaluate during dose initiation and titration. Avoid use of oxymorphone hydrochloride extended-release tablets in patients with circulatory shock. (5.11)
- Risks of Use in Patients with Increased Intracranial Pressure, Brain Tumors, Head Injury, or Impaired Consciousness: Monitor for sedation and respiratory depression. Avoid use of Oxymorphone Hydrochloride Extended-Release Tablets in patients with impaired consciousness or coma. (5.12)

6 ADVERSE REACTIONS

Adverse reactions in ≥2% of patients in placebo-controlled trials: nausea, constipation, dizziness, somnolence, vomiting, pruritus, headache, sweating increased, dry mouth, sedation, diarrhea, insomnia, fatigue, appetite decreased, and abdominal pain. (6.1)

To report SUSPECTED ADVERSE REACTIONS, contact Amneal Pharmaceuticals at 1-877-835-5472 or FDA at 1-800-FDA-1088 or www.fda.gov/medwatch.

7 DRUG INTERACTIONS

- Serotonergic Drugs: Concomitant use may result in serotonin syndrome. Discontinue Oxymorphone Hydrochloride Extended-Release Tablets if serotonin syndrome is suspected. (7)
- Mixed Agonist/Antagonist and Partial Agonist Opioid Analgesics: Avoid use with Oxymorphone Hydrochloride Extended-Release Tablets because they may reduce analgesic effect of Oxymorphone Hydrochloride Extended-Release Tablets or precipitate withdrawal symptoms. (7)
- Monoamine Oxidase Inhibitors (MAOIs): Can potentiate the effects of oxymorphone. Avoid concomitant use in patients receiving MAOIs or within 14 days of stopping treatment with an MAOI. (7)

8 USE IN SPECIFIC POPULATIONS

- Pregnancy: May cause fetal harm. (8.1)
- Lactation: Not recommended. (8.2)

FULL PRESCRIBING INFORMATION

WARNING: SERIOUS AND LIFE-THREATENING RISKS FROM USE OF OXYMORPHONE HYDROCHLORIDE EXTENDED-RELEASE TABLETS

Addiction, Abuse, and Misuse

Because the use of Oxymorphone Hydrochloride Extended-Release Tablets exposes patients and other users to the risks of opioid addiction, abuse, and misuse, which can lead to overdose and death, assess each patient’s risk prior to prescribing and reassess all patients regularly for the development of these behaviors and conditions [see Warnings and Precautions (5.1)].

Life-Threatening Respiratory Depression

Serious, life-threatening, or fatal respiratory depression may occur with use of Oxymorphone Hydrochloride Extended-Release Tablets, especially during initiation or following a dosage increase. To reduce the risk of respiratory depression, proper dosing and titration of Oxymorphone Hydrochloride Extended-Release Tablets are essential. Instruct patients to swallow Oxymorphone Hydrochloride Extended-Release Tablets whole; crushing, chewing, or dissolving Oxymorphone Hydrochloride Extended-Release Tablets can cause rapid release and absorption of a potentially fatal dose of oxymorphone [see Dosage and Administration (2.1) and Warnings and Precautions (5.2)].

Accidental Ingestion

Accidental ingestion of even one dose of Oxymorphone Hydrochloride Extended-Release Tablets, especially by children, can result in a fatal overdose of oxymorphone [see Warnings and Precautions (5.2)].

Interaction with Alcohol

Instruct patients not to consume alcoholic beverages or use prescription or non-prescription products that contain alcohol while taking Oxymorphone Hydrochloride Extended-Release Tablets. The co-ingestion of alcohol with Oxymorphone Hydrochloride Extended-Release Tablets may result in increased plasma levels and a potentially fatal overdose of oxymorphone [see Warnings and Precautions (5.2, 5.3)].

Risks From Concomitant Use with Benzodiazepines or Other CNS Depressants

Concomitant use of opioids with benzodiazepines or other central nervous system (CNS) depressants, including alcohol, may result in profound sedation, respiratory depression, coma, and death. Reserve concomitant prescribing of Oxymorphone Hydrochloride Extended-Release Tablets and benzodiazepines or other CNS depressants for use in patients for whom alternative treatment options are inadequate [see Warnings and Precautions (5.3), Drug Interactions (7)].

Neonatal Opioid Withdrawal Syndrome (NOWS)

Advise pregnant women using opioids for an extended period of time of the risk of Neonatal Opioid Withdrawal Syndrome, which may be life-threatening if not recognized and treated. Ensure that management by neonatology experts will be available at delivery [see Warnings and Precautions (5.4)].

Opioid Analgesic Risk Evaluation and Mitigation Strategy (REMS)

Healthcare providers are strongly encouraged to complete a REMS-compliant education program and to counsel patients and caregivers on serious risks, safe use, and the importance of reading the Medication Guide with each prescription [see Warnings and Precautions (5.5)].

1 INDICATIONS AND USAGE

Oxymorphone Hydrochloride Extended-Release Tablets are indicated for the management of severe and persistent pain that requires an opioid analgesic and that cannot be adequately treated with alternative options, including immediate-release opioids.

Limitations of Usage

- Because of the risks of addiction, abuse, misuse, overdose and death, which can occur at any dosage or duration and persist over the course of therapy [see Warnings and Precautions (5.1)], reserve opioid analgesics, including Oxymorphone Hydrochloride Extended-Release Tablets, for use in patients for whom alternative treatment options are ineffective, not tolerated, or would be otherwise inadequate to provide sufficient management of pain.
- Oxymorphone Hydrochloride Extended-Release Tablets are not indicated as an as-needed (prn) analgesic.

2 DOSAGE AND ADMINISTRATION

2.1 Important Dosage and Administration Instructions

- Oxymorphone Hydrochloride Extended-Release Tablets should be prescribed only by healthcare professionals who are knowledgeable about the use of extended-release/long-acting opioids and how to mitigate the associated risks.
- Patients considered opioid tolerant are those taking, for one week or longer, at least 60 mg oral morphine per day, 25 mcg transdermal fentanyl per hour, 30 mg oral oxycodone per day, 8 mg oral hydromorphone per day, 25 mg oral oxymorphone per day, 60 mg oral hydrocodone per day, or an equianalgesic dose of another opioid.

- Use the lowest effective dosage for the shortest duration of time consistent with individual patient treatment goals [see Warnings and Precautions (5)]. Because the risk of overdose increases as opioid doses increase, reserve titration to higher doses of Oxymorphone Hydrochloride Extended-Release Tablets for patients in whom lower doses are insufficiently effective and in whom the expected benefits of using a higher dose opioid clearly outweigh the substantial risks.
- Initiate the dosing regimen for each patient individually, taking into account the patient’s underlying cause and severity of pain, prior analgesic treatment and response, and risk factors for addiction, abuse, and misuse [see Warnings and Precautions (5.1)].

- Respiratory depression can occur at any time during opioid therapy, especially when initiating and following dosage increases with Oxymorphone Hydrochloride Extended-Release Tablets. Consider this risk when selecting an initial dose and when making dose adjustments [see Warnings and Precautions (5.2)].
- Oxymorphone Hydrochloride Extended-Release Tablets are administered orally twice daily (every 12 hours).
- Instruct patients to swallow Oxymorphone Hydrochloride Extended-Release Tablets whole. Crushing, chewing, or dissolving Oxymorphone Hydrochloride Extended-Release Tablets will result in uncontrolled delivery of oxymorphone and can lead to overdose or death [see Warnings and Precautions (5.2)].
- Administer on an empty stomach, at least 1 hour prior to or 2 hours after eating.

2.2 Patient Access to an Opioid Overdose Reversal Agent for the Emergency Treatment of Opioid Overdose

Inform patients and caregivers about opioid overdose reversal agents (e.g., naloxone, nalmefene). Discuss the importance of having access to an opioid overdose reversal agent, especially if the patient has risk factors for overdose (e.g., concomitant use of CNS depressants, a history of opioid use disorder, or prior opioid overdose) or if there are household members (including children) or other close contacts at risk for accidental ingestion or opioid overdose. The presence of risk factors for overdose should not prevent the management of pain in any patient [see Warnings and Precautions (5.1, 5.2, 5.3)].

Discuss the options for obtaining an opioid overdose reversal agent (e.g., prescription, over-the-counter, or as part of a community-based program) [see Warnings and Precautions (5.2)].

There are important differences among the opioid overdose reversal agents, such as route of administration, product strength, approved patient age range, and pharmacokinetics. Be familiar with these differences, as outlined in the approved labeling for those products, prior to recommending or prescribing such an agent.

2.3 Initial Dosing

It is safer to underestimate a patient’s 24-hour oral morphine dosage and provide rescue medication (e.g., immediate-release opioid) than to overestimate the 24-hour oral morphine dosage and manage an adverse reaction due to an overdose. While useful tables of opioid equivalents are readily available, there is inter-patient variability in the potency of opioid drugs and opioid formulations. Frequently reevaluate patients for signs and symptoms of opioid withdrawal and for signs of oversedation/toxicity after converting patients to Oxymorphone Hydrochloride Extended-Release Tablets.

Use of Oxymorphone Hydrochloride Extended-Release Tablets in Patients who are not Opioid Tolerant

The starting dose for patients who are not opioid tolerant is Oxymorphone Hydrochloride Extended-Release Tablets 5 mg orally every 12 hours.

Use of higher starting doses in patients who are not opioid tolerant may cause fatal respiratory depression [see Warnings and Precautions (5.2)].

Conversion from Other Oral Opioids to Oxymorphone Hydrochloride Tablets to Oxymorphone Hydrochloride Extended-Release Tablets

Patients receiving oral oxymorphone hydrochloride tablets may be converted to Oxymorphone Hydrochloride Extended-Release Tablets by administering half the patient’s total daily oral oxymorphone hydrochloride tablets dose as Oxymorphone Hydrochloride Extended-Release Tablets, every 12 hours.

Conversion from Parenteral Oxymorphone to Oxymorphone Hydrochloride Extended-Release Tablets

The absolute oral bioavailability of Oxymorphone Hydrochloride Extended-Release Tablets are approximately 10%. Convert patients receiving parenteral oxymorphone to Oxymorphone Hydrochloride Extended-Release Tablets by administering 10 times the patient’s total daily parenteral oxymorphone dose as Oxymorphone Hydrochloride Extended-Release Tablets in two equally divided doses (e.g., [IV dose x 10] divided by 2). Due to patient variability with regards to opioid analgesic response, upon conversion monitor patients closely to evaluate for adequate analgesia and side effects.

Conversion from Other Oral Opioid Analgesics to Oxymorphone Hydrochloride Extended-Release Tablets

When Oxymorphone Hydrochloride Extended-Release Tablets therapy is initiated, discontinue all other opioid analgesics other than those used on an as needed basis for breakthrough pain when appropriate.

In an Oxymorphone Hydrochloride Extended-Release Tablets clinical trial with an open-label titration period, patients were converted from their prior opioid to Oxymorphone Hydrochloride Extended-Release Tablets using Table 1 as a guide for the initial Oxymorphone Hydrochloride Extended-Release Tablets dose.

Consider the following when using the information in the below Table 1:

- This is not a table of equianalgesic doses.
- The conversion factors in this table are only for the conversion from one of the listed oral opioid analgesics to Oxymorphone Hydrochloride Extended-Release Tablets.
- This table cannot be used to convert from Oxymorphone Hydrochloride Extended-Release Tablets to another opioid. Doing so will result in an over-estimation of the dose of the new opioid and may result in fatal overdose.

Table 1: CONVERSION FACTORS TO OXYMORPHONE HYDROCHLORIDE EXTENDED-RELEASE TABLETS

Prior Oral Opioid | Approximate Oral Conversion Factor
Oxymorphone | 1
Hydrocodone | 0.5
Oxycodone | 0.5
Methadone | 0.5
Morphine | 0.333

To calculate the estimated Oxymorphone Hydrochloride Extended-Release Tablet dose using the above table:

- For patients on a single opioid, sum the current total daily dose of the opioid and then multiply the total daily dose by the conversion factor to calculate the approximate oral (active opioid) daily dose.
- For patients on a regimen of more than one opioid, calculate the approximate oral (active opioid) dose for each opioid and sum the totals to obtain the approximate total (active opioid) daily dose.
- For patients on a regimen of fixed-ratio opioid/non-opioid analgesic products, use only the opioid component of these products in the conversion.

Always round the dose down, if necessary, to the appropriate Oxymorphone Hydrochloride Extended-Release Tablet strength(s) available.

Example conversion from a single opioid to Oxymorphone Hydrochloride Extended-Release Tablets:

Step 1: Sum the total daily dose of the opioid oxycodone 20 mg twice daily 20 mg former opioid 2 times daily = 40 mg total daily dose of former opioid

Step 2: Calculate the approximate equivalent dose of oral (active opioid) based on the total daily dose of the current opioid using Table 1 40 mg total daily dose of former opioid x 0.5 mg Conversion Factor = 20 mg of oral (active opioid) daily

Step 3: Calculate the approximate starting dose of Oxymorphone Hydrochloride Extended-Release Tablets to be given every 12 hours. Round down, if necessary, to the appropriate Oxymorphone Hydrochloride Extended-Release Tablets strengths available.

10 mg Oxymorphone Hydrochloride Extended-Release Tablets every 12 hours

Conversion from Methadone to Oxymorphone Hydrochloride Extended-Release Tablets

Regular evaluation is of particular importance when converting from methadone to other opioid agonists. The ratio between methadone and other opioid agonists may vary widely as a function of previous dose exposure. Methadone has a long half-life and can accumulate in the plasma.

2.4 Titration and Maintenance of Therapy

Individually titrate Oxymorphone Hydrochloride Extended-Release Tablets to a dose that provides adequate analgesia and minimizes adverse reactions. Continually reevaluate patients receiving Oxymorphone Hydrochloride Extended-Release Tablets to assess the maintenance of pain control, signs and symptoms of opioid withdrawal, and other adverse reactions, as well as to reassess for the development of addiction, abuse, and misuse [see Warnings and Precautions (5.1, 5.15)]. Frequent communication is important among the prescriber, other members of the healthcare team, the patient, and the caregiver/family during periods of changing analgesic requirements, including initial titration. During use of opioid therapy for an extended period of time, periodically reassess the continued need for the use of opioid analgesics.

Patients who experience breakthrough pain may require a dose increase of Oxymorphone Hydrochloride Extended-Release Tablets, or may need rescue medication with an appropriate dose of an immediate-release analgesic.

If the level of pain increases after dose stabilization, attempt to identify the source of increased pain before increasing Oxymorphone Hydrochloride Extended-Release Tablets dose.

If after increasing the dosage, unacceptable opioid-related adverse reactions are observed (including an increase in pain after dosage increase), consider reducing the dosage [see Warnings and Precautions (5)]. Adjust the dose to obtain an appropriate balance between management of pain and opioid-related adverse reactions.

Because steady-state plasma concentrations are approximated within 3 days, Oxymorphone Hydrochloride Extended-Release Tablets dosage adjustments, preferably at increments of 5 mg to 10 mg every 12 hours, may be done every 3 to 7 days.

2.5 Safe Reduction or Discontinuation of Oxymorphone Hydrochloride Extended-Release Tablets

Do not rapidly reduce or abruptly discontinue Oxymorphone Hydrochloride Extended-Release Tablets in patients who may be physically dependent on opioids. Rapid reduction or abrupt discontinuation of opioid analgesics in patients who are physically dependent on opioids has resulted in serious withdrawal symptoms, uncontrolled pain, and suicide. Rapid reduction or abrupt discontinuation has also been associated with attempts to find other sources of opioid analgesics, which may be confused with drug-seeking for abuse. Patients may also attempt to treat their pain or withdrawal symptoms with illicit opioids, such as heroin, and other substances.

When a decision has been made to decrease the dose or discontinue therapy in an opioid-dependent patient taking Oxymorphone Hydrochloride Extended-Release Tablets, there are a variety of factors that should be considered, including the total daily dose of opioid (including Oxymorphone Hydrochloride Extended-Release Tablets) the patient has been taking, the duration of treatment, the type of pain being treated, and the physical and psychological attributes of the patient. It is important to ensure ongoing care of the patient and to agree on an appropriate tapering schedule and follow-up plan so that patient and provider goals and expectations are clear and realistic. When opioid analgesics are being discontinued due to a suspected substance use disorder, evaluate and treat the patient, or refer for evaluation and treatment of the substance use disorder. Treatment should include evidence-based approaches, such as medication assisted treatment of opioid use disorder. Complex patients with comorbid pain and substance use disorders may benefit from referral to a specialist.

There are no standard opioid tapering schedules that are suitable for all patients. Good clinical practice dictates a patient-specific plan to taper the dose of the opioid gradually. For patients on Oxymorphone Hydrochloride Extended-Release Tablets who are physically opioid-dependent, initiate the taper by a small enough increment (e.g., no greater than 10% to 25% of the total daily dose) to avoid withdrawal symptoms, and proceed with dose-lowering at an interval of every 2 to 4 weeks. Patients who have been taking opioids for briefer periods of time may tolerate a more rapid taper.

It may be necessary to provide the patient with lower dosage strengths to accomplish a successful taper. Reassess the patient frequently to manage pain and withdrawal symptoms, should they emerge. Common withdrawal symptoms include restlessness, lacrimation, rhinorrhea, yawning, perspiration, chills, myalgia, and mydriasis. Other signs and symptoms also may develop, including irritability, anxiety, backache, joint pain, weakness, abdominal cramps, insomnia, nausea, anorexia, vomiting, diarrhea, or increased blood pressure, respiratory rate, or heart rate. If withdrawal symptoms arise, it may be necessary to pause the taper for a period of time or raise the dose of the opioid analgesic to the previous dose, and then proceed with a slower taper. In addition, evaluate patients for any changes in mood, emergence of suicidal thoughts, or use of other substances.

When managing patients taking opioid analgesics, particularly those who have been treated for an extended period of time, and/or with high doses for chronic pain, ensure that a multimodal approach to pain management, including mental health support (if needed), is in place prior to initiating an opioid analgesic taper. A multimodal approach to pain management may optimize the treatment of chronic pain, as well as assist with the successful tapering of the opioid analgesic [see Warnings and Precautions (5.15) and Drug Abuse and Dependence (9.3)].

2.6 Dosage Modification in Patients with Mild Hepatic Impairment

Oxymorphone Hydrochloride Extended-Release Tablets are contraindicated in patients with moderate or severe hepatic impairment.

In patients with mild hepatic impairment who are not opioid tolerant, initiate treatment with the 5 mg dose. For patients on prior opioid therapy, start Oxymorphone Hydrochloride Extended-Release Tablets at 50% lower than the starting dose for a patient with normal hepatic function on prior opioids and titrate slowly. Regularly evaluate patients for signs of respiratory or central nervous system depression [see Warnings and Precautions (5.2), Use in Specific Populations (8.6) and Clinical Pharmacology (12.3)].

2.7 Dosage Modifications in Patients with Renal Impairment

In patients with creatinine clearance rates less than 50 mL/min, start Oxymorphone Hydrochloride Extended-Release Tablets in patients who are not opioid tolerant with the 5 mg dose. For patients on prior opioid therapy, start Oxymorphone Hydrochloride Extended-Release Tablets at 50% lower than the starting dose for a patient with normal renal function on prior opioids and titrate slowly. Regularly evaluate patients for signs of respiratory or central nervous system depression [see Warnings and Precautions (5.2), Use in Specific Populations (8.7) and Clinical Pharmacology (12.3)].

2.8 Dosage Modifications in Geriatric Patients

The steady-state plasma concentrations of oxymorphone are higher in elderly subjects than in young subjects. Initiate dosing with Oxymorphone Hydrochloride Extended-Release Tablets in patients 65 years of age and over using the 5 mg dose and regularly evaluate for signs of respiratory and central nervous system depression when initiating and titrating Oxymorphone Hydrochloride Extended-Release Tablets to adequate analgesia [see Warnings and Precautions (5.2), Use in Specific Populations (8.5) and Clinical Pharmacology (12.3)]. For patients on prior opioid therapy, start Oxymorphone Hydrochloride Extended-Release Tablets at 50% lower than the starting dose for a younger patient on prior opioids and titrate slowly.

3 DOSAGE FORMS AND STRENGTHS

Oxymorphone Hydrochloride Extended-Release Tablets USP, 5 mg dosage form is a purple, round, film-coated extended-release tablet debossed with “G71” on one side and blank on the other side.

Oxymorphone Hydrochloride Extended-Release Tablets USP, 7.5 mg dosage form is a gray, round, film-coated extended-release tablet debossed with “G75” on one side and blank on the other side.

Oxymorphone Hydrochloride Extended-Release Tablets USP, 10 mg dosage form is an orange, round, film-coated extended-release tablet debossed with “G72” on one side and blank on the other side.

Oxymorphone Hydrochloride Extended-Release Tablets USP, 15 mg dosage form is a white, round, film-coated extended-release tablet debossed with “G76” on one side and blank on the other side.

Oxymorphone Hydrochloride Extended-Release Tablets USP, 20 mg dosage form is a green, round, film-coated extended-release tablet debossed with “G73” on one side and blank on the other side.

Oxymorphone Hydrochloride Extended-Release Tablets USP, 30 mg dosage form is a brown, round, film-coated extended-release tablet debossed with “G77” on one side and blank on the other side.

Oxymorphone Hydrochloride Extended-Release Tablets USP, 40 mg dosage form is an orange, round, film-coated extended-release tablet debossed with “G74” on one side and blank on the other side.

4 CONTRAINDICATIONS

Oxymorphone Hydrochloride Extended-Release Tablets are contraindicated in patients with:

- Significant respiratory depression [see Warnings and Precautions (5.7)]
- Acute or severe bronchial asthma in an unmonitored setting or in the absence of resuscitative equipment [see Warnings and Precautions (5.7)]
- Hypersensitivity (e.g., anaphylaxis) to oxymorphone, any other ingredients in Oxymorphone Hydrochloride Extended-Release Tablets [see Warnings and Precautions (5.8) and Adverse Reactions (6)].
- Moderate and severe hepatic impairment [see Warnings and Precautions (5.10), Clinical Pharmacology (12.3)]
- Known or suspected gastrointestinal obstruction, including paralytic ileus [see Warnings and Precautions (5.13)]

5 WARNINGS AND PRECAUTIONS

5.1 Addiction, Abuse, and Misuse

Oxymorphone Hydrochloride Extended-Release Tablet contains, oxymorphone, a Schedule II controlled substance. As an opioid, Oxymorphone Hydrochloride Extended-Release Tablets exposes users to the risks of addiction, abuse, and misuse.

Although the risk of addiction in any individual is unknown, it can occur in patients appropriately prescribed Oxymorphone Hydrochloride Extended-Release Tablets. Addiction can occur at recommended doses and if the drug is misused or abused. The risk of opioid-related overdose or overdose-related death is increased with higher opioid doses, and this risk persists over the course of therapy. In postmarketing studies, addiction, abuse, misuse, and fatal and non-fatal opioid overdose were observed in patients with long-term opioid use [see Adverse Reactions (6.2)].

Assess each patient’s risk for opioid addiction, abuse, or misuse prior to prescribing Oxymorphone Hydrochloride Extended-Release Tablets and reassess all patients receiving Oxymorphone Hydrochloride Extended-Release Tablets for the development of these behaviors and conditions. Risks are increased in patients with a personal or family history of substance abuse (including drug or alcohol abuse or addiction) or mental illness (e.g., major depression). The potential for these risks should not, however, prevent the proper management of pain in any given patient. Patients at increased risk may be prescribed opioids such as Oxymorphone Hydrochloride Extended-Release Tablets, but use in such patients necessitates intensive counseling about the risks and proper use of Oxymorphone Hydrochloride Extended-Release Tablets along with frequent reevaluation for signs of addiction, abuse, and misuse. Consider recommending or prescribing an opioid overdose reversal agent [see Dosage and Administration (2.2) and Warnings and Precautions (5.2)].

Abuse, or misuse of Oxymorphone Hydrochloride Extended-Release Tablets by crushing, chewing, snorting, or injecting the dissolved product will result in the uncontrolled delivery of the oxymorphone and can result in overdose and death [see Overdosage (10)].

Opioids are sought for nonmedical use and are subject to diversion from legitimate prescribed use. Consider these risks when prescribing or dispensing Oxymorphone Hydrochloride Extended-Release Tablets. Strategies to reduce these risks include prescribing the drug in the smallest appropriate quantity and advising the patient on careful storage of the drug during the course of treatment and proper disposal of unused drug. Contact local state professional licensing board or state-controlled substances authority for information on how to prevent and detect abuse or diversion of this product.

5.2 Life-Threatening Respiratory Depression

Serious, life-threatening, or fatal respiratory depression has been reported with the use of opioids, even when used as recommended. Respiratory depression from opioid use, if not immediately recognized and treated, may lead to respiratory arrest and death. Management of respiratory depression may include close observation, supportive measures, and use of opioid overdose reversal agents, depending on the patient’s clinical status [see Overdosage (10)]. Carbon dioxide (CO2) retention from opioid-induced respiratory depression can exacerbate the sedating effects of opioids.

While serious, life-threatening, or fatal respiratory depression can occur at any time during the use of Oxymorphone Hydrochloride Extended-Release Tablets, the risk is greatest during the initiation of therapy or following a dose increase.

To reduce the risk of respiratory depression, proper dosing and titration of Oxymorphone Hydrochloride Extended-Release Tablets are essential [see Dosage and Administration (2)]. Overestimating the Oxymorphone Hydrochloride Extended-Release Tablets dosage when converting patients from another opioid product can result in fatal overdose with the first dose.

Accidental ingestion of even one dose of Oxymorphone Hydrochloride Extended-Release Tablets, especially by children, can result in respiratory depression and death due to an overdose of oxymorphone.

Educate patients and caregivers on how to recognize respiratory depression and emphasize the importance of calling 911 or getting emergency medical help right away in the event of a known or suspected overdose.

Opioids can cause sleep-related breathing disorders including central sleep apnea (CSA) and sleep-related hypoxemia. Opioid use increases the risk of CSA in a dose-dependent fashion. In patients who present with CSA, consider decreasing the opioid dosage using best practices for opioid taper [see Dosage and Administration (2.5)].

Patient Access to an Opioid Overdose Reversal Agent for the Emergency Treatment of Opioid Overdose

Inform patients and caregivers about opioid overdose reversal agents (e.g., naloxone, nalmefene). Discuss the importance of having access to an opioid overdose reversal agent, especially if the patient has risk factors for overdose (e.g., concomitant use of CNS depressants, a history of opioid use disorder, or prior opioid overdose) or if there are household members (including children) or other close contacts at risk for accidental ingestion or opioid overdose. The presence of risk factors for overdose should not prevent the management of pain in any patient [see Warnings and Precautions (5.1, 5.3)].

Discuss the options for obtaining an opioid overdose reversal agent (e.g., prescription, over-the-counter, or as part of a community-based program).

There are important differences among the opioid overdose reversal agents, such as route of administration, product strength, approved patient age range, and pharmacokinetics. Be familiar with these differences, as outlined in the approved labeling for those products, prior to recommending or prescribing such an agent.

Educate patients and caregivers on how to recognize respiratory depression, and how to use an opioid overdose reversal agent for the emergency treatment of opioid overdose. Emphasize the importance of calling 911 or getting emergency medical help, even if an opioid overdose reversal agent is administered [see Dosage and Administration (2.2), Warnings and Precautions (5.1, 5.7), Overdosage (10)].

5.3 Risks from Concomitant Use with Benzodiazepines or Other CNS Depressants

Patients must not consume alcoholic beverages or prescription or non-prescription products containing alcohol while on Oxymorphone Hydrochloride Extended-Release Tablets therapy. The co-ingestion of alcohol with Oxymorphone Hydrochloride Extended-Release Tablets may result in increased plasma oxymorphone levels and a potentially fatal overdose of oxymorphone [see Clinical Pharmacology (12.3)].

Profound sedation, respiratory depression, coma, and death may result from the concomitant use of Oxymorphone Hydrochloride Extended-Release Tablets with benzodiazepines and/or other CNS depressants, including alcohol (e.g., non-benzodiazepine sedatives/hypnotics, anxiolytics, tranquilizers, muscle relaxants, general anesthetics, antipsychotics, gabapentinoids [gabapentin or pregabalin], and other opioids). Because of these risks, reserve concomitant prescribing of these drugs for use in patients for whom alternative treatment options are inadequate.

Observational studies have demonstrated that concomitant use of opioid analgesics and benzodiazepines increases the risk of drug-related mortality compared to use of opioid analgesics alone. Because of similar pharmacological properties, it is reasonable to expect similar risk with the concomitant use of other CNS depressant drugs with opioid analgesics [see Drug Interactions (7)].

If the decision is made to prescribe a benzodiazepine or other CNS depressant concomitantly with an opioid analgesic, prescribe the lowest effective dosages and minimum durations of concomitant use. In patients already receiving an opioid analgesic, prescribe a lower initial dose of the benzodiazepine or other CNS depressant than indicated in the absence of an opioid, and titrate based on clinical response. If an opioid analgesic is initiated in a patient already taking a benzodiazepine or other CNS depressant, prescribe a lower initial dose of the opioid analgesic, and titrate based on clinical response. Inform patients and caregivers of this potential interaction, educate them on the signs and symptoms of respiratory depression (including sedation).

If concomitant use is warranted, consider recommending or prescribing an opioid overdose reversal agent [see Dosage and Administration (2.2), Warnings and Precautions (5.2) and Overdosage (10)].

Advise both patients and caregivers about the risks of respiratory depression and sedation when Oxymorphone Hydrochloride Extended-Release Tablets are used with benzodiazepines or other CNS depressants (including alcohol and illicit drugs). Advise patients not to drive or operate heavy machinery until the effects of concomitant use of the benzodiazepine or other CNS depressants have been determined. Screen patients for risk of substance use disorders, including opioid abuse and misuse, and warn them of the risk for overdose and death associated with the use of additional CNS depressants including alcohol and illicit drugs [see Drug Interactions (7)].

5.4 Neonatal Opioid Withdrawal Syndrome

Use of Oxymorphone Hydrochloride Extended-Release Tablets for an extended period of time during pregnancy can result in withdrawal in the neonate. Neonatal opioid withdrawal syndrome, unlike opioid withdrawal syndrome in adults, may be life-threatening if not recognized and treated, and requires management according to protocols developed by neonatology experts. Observe newborns for signs of neonatal opioid withdrawal syndrome and manage accordingly. Advise pregnant women using opioids for an extended period of time of the risk of neonatal opioid withdrawal syndrome and ensure that appropriate treatment will be available [see Use in Specific Populations (8.1)].

5.5 Opioid Analgesic Risk Evaluation and Mitigation Strategy (REMS)

To ensure that the benefits of opioid analgesics outweigh the risks of addiction, abuse, and misuse, the Food and Drug Administration (FDA) has required a Risk Evaluation and Mitigation Strategy (REMS) for these products. Under the requirements of the REMS, drug companies with approved opioid analgesic products must make REMS-compliant education programs available to healthcare providers. Healthcare providers are strongly encouraged to do all of the following:

- Complete a REMS-compliant education program offered by an accredited provider of continuing education (CE) or another education program that includes all the elements of the FDA Education Blueprint for Health Care Providers Involved in the Management or Support of Patients with Pain.
- Discuss the safe use, serious risks, and proper storage and disposal of opioid analgesics with patients and/or their caregivers every time these medicines are prescribed. The Patient Counseling Guide (PCG) can be obtained at this link: www.fda.gov/OpioidAnalgesicREMSPCG.
- Emphasize to patients and their caregivers the importance of reading the Medication Guide that they will receive from their pharmacist every time an opioid analgesic is dispensed to them.
- Consider using other tools to improve patient, household, and community safety, such as patient-prescriber agreements that reinforce patient-prescriber responsibilities.

To obtain further information on the opioid analgesic REMS and for a list of accredited REMS CME/CE, call 1-800-503-0784, or log on to www.opioidanalgesicrems.com. The FDA Blueprint can be found at www.fda.gov/OpioidAnalgesicREMSBlueprint.

5.6 Opioid-Induced Hyperalgesia and Allodynia

Opioid-Induced Hyperalgesia (OIH) occurs when an opioid analgesic paradoxically causes an increase in pain, or an increase in sensitivity to pain. This condition differs from tolerance, which is the need for increasing doses of opioids to maintain a defined effect [see Dependence (9.3)]. Symptoms of OIH include (but may not be limited to) increased levels of pain upon opioid dosage increase, decreased levels of pain upon opioid dosage decrease, or pain from ordinarily non-painful stimuli (allodynia). These symptoms may suggest OIH only if there is no evidence of underlying disease progression, opioid tolerance, opioid withdrawal, or addictive behavior.

Cases of OIH have been reported, both with short-term and longer-term use of opioid analgesics. Though the mechanism of OIH is not fully understood, multiple biochemical pathways have been implicated. Medical literature suggests a strong biologic plausibility between opioid analgesics and OIH and allodynia. If a patient is suspected to be experiencing OIH, carefully consider appropriately decreasing the dose of the current opioid analgesic or opioid rotation (safely switching the patient to a different opioid moiety) [see Dosage and Administration (2.5) and Warnings and Precautions (5.15)].

5.7 Life-Threatening Respiratory Depression in Patients with Chronic Pulmonary Disease or in Elderly, Cachectic, or Debilitated Patients

The use of Oxymorphone Hydrochloride Extended-Release Tablets in patients with acute or severe bronchial asthma in an unmonitored setting or in the absence of resuscitative equipment is contraindicated.

Patients with Chronic Pulmonary Disease: Oxymorphone Hydrochloride Extended-Release Tablets treated patients with significant chronic obstructive pulmonary disease or cor pulmonale, and those with a substantially decreased respiratory reserve, hypoxia, hypercapnia, or pre-existing respiratory depression are at increased risk of decreased respiratory drive including apnea, even at recommended dosages of Oxymorphone Hydrochloride Extended-Release Tablets [see Warnings and Precautions (5.2)].

Elderly, Cachectic, or Debilitated Patients: Life-threatening respiratory depression is more likely to occur in elderly, cachectic, or debilitated patients because they may have altered pharmacokinetics or altered clearance compared to younger, healthier patients [see Warnings and Precautions (5.2)].

Regularly evaluate patients, particularly when initiating and titrating Oxymorphone Hydrochloride Extended-Release Tablets and when Oxymorphone Hydrochloride Extended-Release Tablets are given concomitantly with other drugs that depress respiration [see Warnings and Precautions (5.2, 5.3) and Drug Interactions (7)]. Alternatively, consider the use of non-opioid analgesics in these patients.

5.8 Anaphylaxis, Angioedema, and Other Hypersensitivity Reactions

Potentially life-threatening hypersensitivity reactions, including anaphylaxis and angioedema, have occurred in patients treated with Oxymorphone Hydrochloride Extended-Release Tablets in the postmarket setting. The most commonly described clinical features in these reports were swelling of the face, eyes, mouth, lips, tongue, hands, and/or throat; dyspnea; hives, pruritus, and/or rash; and nausea/vomiting. If anaphylaxis or other hypersensitivity occurs, stop administration of Oxymorphone Hydrochloride Extended-Release Tablets immediately, discontinue Oxymorphone Hydrochloride Extended-Release Tablets permanently, and do not rechallenge with any formulation of oxymorphone. Advise patients to seek immediate medical attention if they experience any symptoms of a hypersensitivity reaction.

5.9 Adrenal Insufficiency

Cases of adrenal insufficiency have been reported with opioid use, more often following greater than one month of use. Presentation of adrenal insufficiency may include non-specific symptoms and signs including nausea, vomiting, anorexia, fatigue, weakness, dizziness, and low blood pressure. If adrenal insufficiency is suspected, confirm the diagnosis with diagnostic testing as soon as possible. If adrenal insufficiency is diagnosed, treat with physiologic replacement doses of corticosteroids. Wean the patient off of the opioid to allow adrenal function to recover and continue corticosteroid treatment until adrenal function recovers. Other opioids may be tried as some cases reported use of a different opioid without recurrence of adrenal insufficiency. The information available does not identify any particular opioids as being more likely to be associated with adrenal insufficiency.

5.10 Use in Patients with Hepatic Impairment

A study of Oxymorphone Hydrochloride Extended-Release Tablets in patients with hepatic disease indicated greater plasma concentrations than those with normal hepatic function [see Clinical Pharmacology (12.3)]. Oxymorphone Hydrochloride Extended-Release Tablets are contraindicated in patients with moderate or severe hepatic impairment. In patients with mild hepatic impairment reduce the starting dose to the lowest dose and regularly evaluate for signs of respiratory and central nervous system depression [see Dosage and Administration (2.6)].

5.11 Severe Hypotension

Oxymorphone Hydrochloride Extended-Release Tablets may cause severe hypotension including orthostatic hypotension and syncope in ambulatory patients. There is an increased risk in patients whose ability to maintain blood pressure has already been compromised by a reduced blood volume or concurrent administration of certain CNS depressant drugs (e.g., phenothiazines or general anesthetics) [see Drug Interactions (7)]. Regularly evaluate these patients for signs of hypotension after initiating or titrating the dosage of Oxymorphone Hydrochloride Extended-Release Tablets. In patients with circulatory shock, Oxymorphone Hydrochloride Extended-Release Tablets may cause vasodilation that can further reduce cardiac output and blood pressure. Avoid the use of Oxymorphone Hydrochloride Extended-Release Tablets in patients with circulatory shock.

5.12 Risks of Use in Patients with Increased Intracranial Pressure, Brain Tumors, Head Injury, or Impaired Consciousness

In patients who may be susceptible to the intracranial effects of CO2 retention (e.g., those with evidence of increased intracranial pressure or brain tumors), Oxymorphone Hydrochloride Extended-Release Tablets may reduce respiratory drive, and the resultant CO2 retention can further increase intracranial pressure. Monitor such patients for signs of sedation and respiratory depression, particularly when initiating therapy with Oxymorphone Hydrochloride Extended-Release Tablets.

Opioids may also obscure the clinical course in a patient with a head injury. Avoid the use of Oxymorphone Hydrochloride Extended-Release Tablets in patients with impaired consciousness or coma.

5.13 Risks of Gastrointestinal Complications

Oxymorphone Hydrochloride Extended-Release Tablets are contraindicated in patients with known or suspected gastrointestinal obstruction, including paralytic ileus.

The oxymorphone in Oxymorphone Hydrochloride Extended-Release Tablets may cause spasm of the sphincter of Oddi. Opioids may cause increases in serum amylase. Regularly evaluate patients with biliary tract disease, including acute pancreatitis, for worsening symptoms.

Cases of opioid-induced esophageal dysfunction (OIED) have been reported in patients taking opioids. The risk of OIED may increase as the dose and/or duration of opioids increases. Regularly evaluate patients for signs and symptoms of OIED (e.g., dysphagia, regurgitation, non-cardiac chest pain) and, if necessary, adjust opioid therapy as clinically appropriate [see Clinical Pharmacology (12.2)].

5.14 Increased Risk of Seizures in Patients with Seizure Disorders

The oxymorphone in Oxymorphone Hydrochloride Extended-Release Tablets may increase the frequency of seizures in patients with seizure disorders and may increase the risk of seizures occurring in other clinical settings associated with seizures. Regularly evaluate patients with a history of seizure disorders for worsened seizure control during Oxymorphone Hydrochloride Extended-Release Tablets therapy.

5.15 Withdrawal

Do not rapidly reduce or abruptly discontinue Oxymorphone Hydrochloride Extended-Release Tablets in a patient physically dependent on opioids. When discontinuing Oxymorphone Hydrochloride Extended-Release Tablets in a physically-dependent patient, gradually taper the dosage. Rapid tapering of oxymorphone in a patient physically dependent on opioids may lead to a withdrawal syndrome and return of pain [see Dosage and Administration (2.5) and Drug Abuse and Dependence (9.3)].

Additionally, avoid the use of mixed agonist/antagonist (e.g., pentazocine, nalbuphine, and butorphanol) and partial agonist (e.g., buprenorphine) analgesics in patients who are receiving a full opioid agonist analgesic, including Oxymorphone Hydrochloride Extended-Release Tablets. In these patients, mixed agonists/antagonist and partial agonist analgesics may reduce the analgesic effect and/or may precipitate withdrawal symptoms [see Drug Interactions (7)].

5.16 Risks of Driving and Operating Machinery

Oxymorphone Hydrochloride Extended-Release Tablets may impair the mental or physical abilities needed to perform potentially hazardous activities such as driving a car or operating machinery. Warn patients not to drive or operate dangerous machinery unless they are tolerant to the effects of Oxymorphone Hydrochloride Extended-Release Tablets and know how they will react to the medication.

6 ADVERSE REACTIONS

The following serious adverse reactions are discussed elsewhere in the labeling:

- Addiction, Abuse, and Misuse [see Warnings and Precautions (5.1)]
- Life-Threatening Respiratory Depression [see Warnings and Precautions (5.2)]
- Interactions with Benzodiazepines or Other CNS Depressants [see Warnings and Precautions (5.3)]
- Neonatal Opioid Withdrawal Syndrome [see Warnings and Precautions (5.4)]
- Opioid-Induced Hyperalgesia and Allodynia [see Warnings and Precautions (5.6)]
- Anaphylaxis and Angioedema [see Warnings and Precautions (5.8)]
- Adrenal Insufficiency [see Warnings and Precautions (5.9)]
- Severe Hypotension [see Warnings and Precautions (5.11)]
- Gastrointestinal Adverse Reactions [see Warnings and Precautions (5.13)]
- Seizures [see Warnings and Precautions (5.14)]
- Withdrawal [see Warnings and Precautions (5.15)]

6.1 Clinical Trial Experience

Because clinical trials are conducted under widely varying conditions, adverse reaction rates observed in the clinical trials of a drug cannot be directly compared to rates in the clinical trials of another drug and may not reflect the rates observed in clinical practice.

The safety of Oxymorphone Hydrochloride Extended-Release Tablets was evaluated in a total of 2011 patients in open-label and controlled clinical trials. The clinical trials enrolled of patients with moderate to severe chronic non-malignant pain, cancer pain, and post-surgical pain. The most common serious adverse events reported with administration of Oxymorphone Hydrochloride Extended-Release Tablets were chest pain, pneumonia and vomiting.

Tables 2 and 3 list the most frequently occurring adverse reactions (in at least 5% of patients) from the placebo-controlled trials in patients with low back pain.

Table 2: Treatment-Emergent Adverse Reactions Reported in ≥5% of Patients During the Open-Label Titration Period and Double-Blind Treatment Period by Preferred Term — Number (%) of Treated Patients (12-Week Study In Patients Not Opioid Tolerant with Low Back Pain)

 | Open-Label Titration Period | Double-Blind Treatment Period
 | Oxymorphone Hydrochloride Extended-Release Tablets | Oxymorphone Hydrochloride Extended-Release Tablets | Placebo
Preferred Term | (N = 325) | (N = 105) | (N = 100)
Constipation | 26% | 7% | 1%
Somnolence | 19% | 2% | 0%
Nausea | 18% | 11% | 9%
Dizziness | 11% | 5% | 3%
Headache | 11% | 4% | 2%
Pruritus | 7% | 3% | 1%

Table 3: Treatment-Emergent Adverse Reactions Reported in ≥5% of Patients During the Open-Label Titration Period and Double-Blind Treatment Period by Preferred Term — Number (%) of Treated Patients (12-Week Study In Opioid-Experienced Patients with Low Back Pain)

 | Open-Label Titration Period | Double-Blind Treatment Period
 | Oxymorphone Hydrochloride Extended-Release Tablets | Oxymorphone Hydrochloride Extended-Release Tablets | Placebo
Preferred Term | (N = 250) | (N = 70) | (N = 72)
Nausea | 20% | 3% | 1%
Constipation | 12% | 6% | 1%
Headache | 12% | 3% | 0%
Somnolence | 11% | 3% | 0%
Vomiting | 9% | 0% | 1%
Pruritus | 8% | 0% | 0%
Dizziness | 6% | 0% | 0%

The Table 4 lists adverse reactions that were reported in at least 2% of patients in placebo-controlled trials (N=5).

Table 4: Adverse Reactions Reported in Placebo-Controlled Clinical Trials with Incidence ≥2% in Patients Receiving Oxymorphone Hydrochloride Extended-Release Tablets

MedDRA Preferred Term | Oxymorphone Hydrochloride Extended-Release Tablets; (N=1,259) | Placebo; (N=461)
Nausea | 33% | 13%
Constipation | 28% | 13%
Dizziness (Excl Vertigo) | 18% | 8%
Somnolence | 17% | 2%
Vomiting | 16% | 4%
Pruritus | 15% | 8%
Headache | 12% | 6%
Sweating increased | 9% | 9%
Dry mouth | 6% | < 1%
Sedation | 6% | 8%
Diarrhea | 4% | 6%
Insomnia | 4% | 2%
Fatigue | 4% | 1%
Appetite decreased | 3% | < 1%
Abdominal pain | 3% | 2%

The common (≥1% to <10%) adverse drug reactions reported at least once by patients treated with Oxymorphone Hydrochloride Extended-Release Tablets in the clinical trials organized by MedDRA’s (Medical Dictionary for Regulatory Activities) System Organ Class and not represented in Table 2 were:

Eye disorders: vision blurred

Gastrointestinal disorders: diarrhea, abdominal pain, dyspepsia

General disorders and administration site conditions: dry mouth, appetite decreased, fatigue, lethargy, weakness, pyrexia, dehydration, weight decreased, edema

Nervous system disorders: insomnia

Psychiatric disorders: anxiety, confusion, disorientation, restlessness, nervousness, depression

Respiratory, thoracic and mediastinal disorders: dyspnea

Vascular disorders: flushing and hypertension

Other less common adverse reactions known with opioid treatment that were seen <1% in the Oxymorphone Hydrochloride Extended-Release Tablet trials include the following: Bradycardia, palpitation, syncope, tachycardia, postural hypotension, miosis, abdominal distention, ileus, hot flashes, allergic reactions, hypersensitivity, urticaria, oxygen saturation decreased, central nervous system depression, depressed level of consciousness, agitation, dysphoria, euphoric mood, hallucination, mental status changes, difficult micturition, urinary retention, hypoxia, respiratory depression, respiratory distress, clamminess, dermatitis, hypotension.

6.2 Post-marketing Experience

The following adverse reactions have been identified during post approval use of opioids. Because these reactions are reported voluntarily from a population of uncertain size, it is not always possible to reliably estimate their frequency or establish a causal relationship to drug exposure.

Nervous system disorder: amnesia, convulsion, memory impairment.

Serotonin syndrome: Cases of serotonin syndrome, a potentially life-threatening condition, have been reported during concomitant use of opioids with serotonergic drugs.

Adrenal insufficiency: Cases of adrenal insufficiency have been reported with opioid use, more often following greater than one month of use.

Anaphylaxis: Anaphylaxis has been reported with ingredients contained in Oxymorphone Hydrochloride Extended-Release Tablets.

Androgen deficiency: Cases of androgen deficiency have occurred with use of opioids for an extended period of time [see Clinical Pharmacology (12)].

Hyperalgesia and Allodynia: Cases of hyperalgesia and allodynia have been reported with opioid therapy of any duration [see Warnings and Precautions (5.6)]

Hypoglycemia: Cases of hypoglycemia have been reported in patients taking opioids. Most reports were in patients with at least one predisposing risk factor (e.g., diabetes).

Opioid-induced esophageal dysfunction (OIED): Cases of OIED have been reported in patients taking opioids, and may occur more frequently in patients taking higher doses of opioids, and/or in patients taking opioids longer term [see Warnings and Precautions (5.13)].

Adverse Reactions from Observational Studies

A prospective, observational cohort study estimated the risks of addiction, abuse, and misuse in patients initiating long-term use of Schedule II opioid analgesics between 2017 and 2021. Study participants included in one or more analyses had been enrolled in selected insurance plans or health systems for at least one year, were free of at least one outcome at baseline, completed a minimum number of follow-up assessments, and either: 1) filled multiple extended-release/long-acting opioid analgesic prescriptions during a 90-day period (n=978); or 2) filled any Schedule II opioid analgesic prescriptions covering at least 70 of 90 days (n=1,244). Those included also had no dispensing of the qualifying opioids in the previous 6 months.

Over 12 months:

- approximately 1% to 6% of participants across the two cohorts newly met criteria for addiction, as assessed with two validated interview-based measures of moderate-to-severe opioid use disorder based on Diagnostic and Statistical Manual of Mental Disorders, Fifth Edition (DSM-5) criteria, and
- approximately 9% and 22% of participants across the two cohorts newly met criteria for prescription opioid abuse and misuse [defined in Drug Abuse and Dependence (9.2)], respectively, as measured with a validated self-reported instrument.

A retrospective, observational cohort study estimated the risk of opioid-involved overdose or opioid overdose-related death in patients with new long-term use of Schedule II opioid analgesics from 2006 through 2016 (n=220,249). Included patients had been enrolled in either one of two commercial insurance programs, one managed care program, or one Medicaid program for at least 9 months. New long-term use was defined as having Schedule II opioid analgesic prescriptions covering at least 70 days’ supply over the 3 months prior to study entry and none during the preceding 6 months. Patients were excluded if they had an opioid-involved overdose in the 9 months prior to study entry. Overdose was measured using a validated medical code-based algorithm with linkage to the National Death Index database. The 5-year cumulative incidence estimates for opioid-involved overdose or opioid overdose-related death ranged from approximately 1.5% to 4% across study sites, counting only the first event during follow-up. Approximately 17% of first opioid overdoses observed over the entire study period (5 to 11 years, depending on the study site) were fatal. Higher baseline opioid dose was the strongest and most consistent predictor of opioid-involved overdose or opioid overdose-related death. Study exclusion criteria may have selected patients at lower risk of overdose, and substantial loss to follow-up (approximately 80%) also may have biased estimates.

The risk estimates from the studies described above may not be generalizable to all patients receiving opioid analgesics, such as those with exposures shorter or longer than the duration evaluated in the studies.

7 DRUG INTERACTIONS

Table 5 includes clinically significant drug interactions with Oxymorphone Hydrochloride Extended-Release Tablets.

Table 5: Clinically Significant Drug Interactions with Oxymorphone Hydrochloride Extended-Release Tablets

Alcohol
Clinical Impact: | The concomitant use of alcohol with Oxymorphone Hydrochloride Extended-Release Tablets can result in an increase of oxymorphone plasma levels and potentially fatal overdose of oxymorphone.
Intervention: | Instruct patients not to consume alcoholic beverages or use prescription or non-prescription products containing alcohol while on Oxymorphone Hydrochloride Extended-Release Tablets therapy [see Warnings and Precautions (5.3) and Clinical Pharmacology (12.3)].
Benzodiazepines and other Central Nervous System (CNS) Depressants
Clinical Impact: | Due to additive pharmacologic effect, the concomitant use of benzodiazepines or other CNS depressants including alcohol, can increase the risk of hypotension, respiratory depression, profound sedation, coma, and death [see Warnings and Precautions (5.3)].
Intervention: | Reserve concomitant prescribing of these drugs for use in patients for whom alternative treatment options are inadequate. Limit dosages and durations to the minimum required. Inform patients and caregivers of this potential interaction and educate them on the signs and symptoms of respiratory depression (including sedation). If concomitant use is warranted, consider recommending or prescribing an opioid overdose reversal agent [see Dosage and Administration (2.2) and Warnings and Precautions (5.1, 5.2, 5.3)].
Examples: | Benzodiazepines and other sedatives/hypnotics, anxiolytics, tranquilizers, muscle relaxants, general anesthetics, antipsychotics, gabapentinoids (gabapentin or pregabalin), other opioids, alcohol.
Serotonergic Drugs
Clinical Impact: | The concomitant use of opioids with other drugs that affect the serotonergic neurotransmitter system has resulted in serotonin syndrome.
Intervention: | If concomitant use is warranted, frequently evaluate the patient, particularly during treatment initiation and dose adjustment. Discontinue Oxymorphone Hydrochloride Extended-Release Tablets if serotonin syndrome is suspected.
Examples: | Selective serotonin reuptake inhibitors (SSRIs), serotonin and norepinephrine reuptake inhibitors (SNRIs), tricyclic antidepressants (TCAs), triptans, 5-HT3 receptor antagonists, drugs that affect the serotonin neurotransmitter system (e.g., mirtazapine, trazodone, tramadol), certain muscle relaxants (i.e., cyclobenzaprine, metaxalone), monoamine oxidase inhibitors (those intended to treat psychiatric disorders and also others, such as linezolid and intravenous methylene blue).
Monoamine Oxidase Inhibitors (MAOIs)
Clinical Impact: | MAOI interactions with opioids may manifest as serotonin syndrome or opioid toxicity (e.g., respiratory depression, coma) [see Warnings and Precautions (5.2)].
Intervention: | The use of Oxymorphone Hydrochloride Extended-Release Tablets are not recommended for patients taking MAOIs or within 14 days of stopping such treatment.
Examples: | phenelzine, tranylcypromine, linezolid
Mixed Agonist/Antagonist and Partial Agonist Opioid Analgesics
Clinical Impact: | May reduce the analgesic effect of Oxymorphone Hydrochloride Extended-Release Tablets and/or precipitate withdrawal symptoms.
Intervention: | Avoid concomitant use.
Examples: | butorphanol, nalbuphine, pentazocine, buprenorphine
Diuretics
Clinical Impact: | Opioids can reduce the efficacy of diuretics by inducing the release of antidiuretic hormone.
Intervention: | Evaluate patients for signs of diminished diuresis and/or effects on blood pressure and increase the dosage of the diuretic as needed.
Muscle Relaxants
Clinical Impact: | Oxymorphone may enhance the neuromuscular blocking action of skeletal muscle relaxants and produce an increased degree of respiratory depression.
Intervention: | Because respiratory depression may be greater than otherwise expected, decrease the dosage of Oxymorphone Hydrochloride Extended-Release Tablets and/or the muscle relaxant as necessary. Due to the risk of respiratory depression with concomitant use of skeletal muscle relaxants and opioids, consider recommending or prescribing an opioid overdose reversal agent [see Dosage and Administration (2.2) and Warnings and Precautions (5.2, 5.3)].
Examples: | cyclobenzaprine, metaxalone
Anticholinergic Drugs
Clinical Impact: | The concomitant use of anticholinergic drugs may increase risk of urinary retention and/or severe constipation, which may lead to paralytic ileus.
Intervention: | Evaluate patients for signs of urinary retention or reduced gastric motility when Oxymorphone Hydrochloride Extended-Release Tablets are used concomitantly with anticholinergic drugs.
Cimetidine
Clinical Impact: | Cimetidine can potentiate opioid-induced respiratory depression.
Intervention: | Evaluate patients for respiratory depression when Oxymorphone Hydrochloride Extended-Release Tablets and cimetidine are used concurrently.

8 USE IN SPECIFIC POPULATIONS

8.1 Pregnancy

Risk Summary

Use of opioid analgesics for an extended period of time during pregnancy may cause neonatal opioid withdrawal syndrome [see Warnings and Precautions (5.4)]. Available data with Oxymorphone Hydrochloride Extended-Release Tablets in pregnant women are insufficient to inform a drug-associated risk for major birth defects and miscarriage.

In animal reproduction studies, reduced postnatal survival of pups and an increased incidence of stillborn pups were observed following oral treatment of pregnant rats with oxymorphone during gestation and through lactation at doses 2.4 and 12 times the human daily dose of 20 mg/day (HDD), respectively. Reduced fetal weights were observed with oral administration of oxymorphone to pregnant rats and rabbits during organogenesis at exposures up to 4.9 and 48.8 times the HDD, respectively [see Data]. Based on animal data, advise pregnant women of the potential risk to a fetus.

The background risk of major birth defects and miscarriage for the indicated population is unknown. All pregnancies have a background risk of birth defect, loss, or other adverse outcomes. In the U.S. general population, the estimated background risk of major birth defects and miscarriage in clinical recognized pregnancies is 2% to 4% and 14% to 20%, respectively.

Clinical Considerations

Fetal/Neonatal adverse reactions

Use of opioid analgesics for an extended period of time during pregnancy for medical or nonmedical purposes can result in physical dependence in the neonate and neonatal opioid withdrawal syndrome shortly after birth. Neonatal opioid withdrawal syndrome presents as irritability, hyperactivity and abnormal sleep pattern, high pitched cry, tremor, vomiting, diarrhea, and failure to gain weight. The onset, duration, and severity of neonatal opioid withdrawal syndrome vary based on the specific opioid used, duration of use, timing and amount of last maternal use, and rate of elimination of the drug by the newborn. Observe newborns for symptoms of neonatal opioid withdrawal syndrome and manage accordingly [see Warnings and Precautions (5.4)].

Labor or delivery

Opioids cross the placenta and may produce respiratory depression and psycho-physiologic effects in neonates. An opioid overdose reversal agent, such as naloxone or nalmefene, must be available for reversal of opioid-induced respiratory depression in the neonate. Oxymorphone Hydrochloride Extended-Release Tablets are not recommended for use in women during and immediately prior to labor, when use of shorter acting analgesics or other analgesic techniques are more appropriate. Opioid analgesics, including Oxymorphone Hydrochloride Extended-Release Tablets, can prolong labor through actions which temporarily reduce the strength, duration, and frequency of uterine contractions. However, this effect is not consistent and may be offset by an increased rate of cervical dilatation, which tends to shorten labor. Monitor neonates exposed to opioid analgesics during labor for signs of excess sedation and respiratory depression.

Data

Animal data

Pregnant rats were treated with oxymorphone hydrochloride from Gestation Day 6 to 17 via oral gavage doses of 5 mg/kg/day, 10 mg/kg/day or 25 mg/kg/day (2.4, 4.9, or 12.2 times the HDD based on body surface area, respectively). Reduced mean fetal weights were observed at 4.9 times the HDD. Maternal toxicity was noted in all treatment groups (reduced food consumption and body weights in all groups and mortality in the high dose group).

Pregnant rabbits were treated with oxymorphone hydrochloride from Gestation Day 7 to 20 via oral gavage doses of 10 mg/kg/day, 25 mg/kg/day or 50 mg/kg/day (9.8, 24.4, or 48.8 times the HDD based on body surface area, respectively). Decreased mean fetal weights were noted at 48.8 times the HDD. Maternal toxicity was noted in all treatment groups (reduced food consumption and body weights).

Pregnant rats were treated with oxymorphone hydrochloride from Gestation Day 6 to Lactation Day 20 via oral gavage doses of 1 mg/kg/day, 5 mg/kg/day, 10 mg/kg/day, or 25 mg/kg/day (0.5, 2.4, 4.9, or 12.2 times the HDD based on body surface area, respectively). Increased neonatal death (postnatal day 0 to 1) was noted at 2.4 times the HDD. Decreased pup survival over the first week of life, reduced pup birth weight, and reduced postnatal weight gain were noted at 4.9 times the HDD. Maternal toxicity was noted in all treatment groups (reduced food consumption and body weights in all groups and mortality in the 10 mg/kg/day and 25 mg/kg/day groups).

In a published study, neural tube defects (exencephaly and cranioschisis) were noted following subcutaneous administration of 153 mg/kg oxymorphone hydrochloride (62.2 times the HDD) on Gestation Day 8 to pregnant hamsters. This dose also produced significant maternal toxicity (20% maternal deaths).

8.2 Lactation

Risk Summary

There is no information regarding the presence of oxymorphone in human milk, the effects on the breastfed infant, or the effects on milk production. Because of the potential for serious adverse reactions, including excess sedation and respiratory depression in a breastfed infant, advise patients that breastfeeding is not recommended during treatment with Oxymorphone Hydrochloride Extended-Release Tablets.

Clinical Considerations

Monitor infants exposed to oxymorphone through breast milk for excess sedation and respiratory depression. Withdrawal symptoms can occur in breastfed infants when maternal administration of an opioid analgesic is stopped, or when breast-feeding is stopped.

8.3 Females and Males of Reproductive Potential

Infertility

Use of opioids for an extended period of time may cause reduced fertility in females and males of reproductive potential. It is not known whether these effects on fertility are reversible [Clinical Pharmacology (12.2) and Nonclinical Toxicology (13.1)].

8.4 Pediatric Use

The safety and effectiveness of Oxymorphone Hydrochloride Extended-Release Tablets in patients below the age of 18 years have not been established. Two open-label studies were conducted in a total of 42 pediatric patients between the ages of 7 to 17 years requiring continuous, around the clock opioid treatment. The available safety and efficacy data were inconclusive for chronic use of Oxymorphone Hydrochloride Extended-Release Tablets. Limited data from one of the studies suggested that Oxymorphone Hydrochloride Extended-Release Tablets is not recommended for post-surgical pain.

8.5 Geriatric Use

Of the total number of subjects in clinical studies of Oxymorphone Hydrochloride Extended-Release Tablets, 27% were 65 and over, while 9% were 75 and over. No overall differences in effectiveness were observed between these subjects and younger subjects. There were several adverse events that were more frequently observed in subjects 65 and over compared to younger subjects. These adverse events included dizziness, somnolence, confusion, and nausea. On average, age greater than 65 years was associated with an increase in oxymorphone AUC and Cmax. Initiate dosing with Oxymorphone Hydrochloride Extended-Release Tablets in patients 65 years of age and over using the 5 mg dose and frequently reevaluate the patient for signs of respiratory and central nervous system depression when initiating and titrating Oxymorphone Hydrochloride Extended-Release Tablets [see Warnings and Precautions (5.2)]. For patients on prior opioid therapy, start at 50% of the starting dose for a younger patient on prior opioids and titrate slowly.

Oxymorphone is known to be substantially excreted by the kidney and the risk of adverse reactions to this drug may be greater in patients with impaired renal function. Because the elderly patients are more likely to have decreased renal function, care should be taken in dose selection, and it may be useful to monitor renal function.

8.6 Hepatic Impairment

Patients with mild hepatic impairment have an increase in oxymorphone bioavailability compared to the subjects with normal hepatic function. In patients who are not opioid tolerant with mild hepatic impairment, initiate Oxymorphone Hydrochloride Extended-Release Tablets using the 5 mg dose and regularly evaluate patients for respiratory and central nervous system depression. Oxymorphone Hydrochloride Extended-Release Tablets are contraindicated for patients with moderate and severe hepatic impairment [see Dosage and Administration (2.6), Contraindications (4), Warnings and Precautions (5.10) and Clinical Pharmacology (12.3)]. For patients on prior opioid therapy, start at the 50% of the dose for that a patient with normal hepatic function on prior opioids and titrate slowly.

8.7 Renal Impairment

Patients with moderate to severe renal impairment were shown to have an increase in oxymorphone bioavailability compared to the subjects with normal renal function [see Clinical Pharmacology (12.3)]. Start patients who are not opioid tolerant with the 5 mg dose of Oxymorphone Hydrochloride Extended-Release Tablets and titrate slowly while regularly evaluating for respiratory and central nervous system depression [see Dosage and Administration (2.6)]. For patients on prior opioid therapy, start at 50% of the dose for a patient with normal renal function on prior opioids and titrate slowly.

9 DRUG ABUSE AND DEPENDENCE

9.1 Controlled Substance

Oxymorphone Hydrochloride Extended-Release Tablets contain oxymorphone, a Schedule II controlled substance.

9.2 Abuse

Oxymorphone Hydrochloride Extended-Release Tablets contain oxymorphone, a substance with a high potential for misuse and abuse, which can lead to the development of substance use disorder, including addiction [see Warnings and Precautions (5.1)].

Misuse is the intentional use, for therapeutic purposes, of a drug by an individual in a way other than prescribed by a healthcare provider or for whom it was not prescribed.

Abuse is the intentional, non-therapeutic use of a drug, even once, for its desirable psychological or physiological effects.

Drug addiction is a cluster of behavioral, cognitive, and physiological phenomena that may include a strong desire to take the drug, difficulties in controlling drug use (e.g., continuing drug use despite harmful consequences, giving a higher priority to drug use than to other activities and obligations), and possible tolerance or physical dependence.

Misuse and abuse of Oxymorphone Hydrochloride Extended-Release Tablets increases risk of overdose, which may lead to central nervous system and respiratory depression, hypotension, seizures, and death. The risk is increased with concurrent abuse of Oxymorphone Hydrochloride Extended-Release Tablets with alcohol and/or other CNS depressants. Abuse of and addiction to opioids in some individuals may not be accompanied by concurrent tolerance and symptoms of physical dependence. In addition, abuse of opioids can occur in the absence of addiction.

All patients treated with opioids require careful and frequent reevaluation for signs of misuse, abuse, and addiction, because use of opioid analgesic products carries the risk of addiction even under appropriate medical use. Patients at high risk of Oxymorphone Hydrochloride Extended-Release Tablets abuse include those with a history of prolonged use of any opioid, including products containing oxymorphone, those with a history of drug or alcohol abuse, or those who use Oxymorphone Hydrochloride Extended-Release Tablets in combination with other abused drugs.

“Drug seeking" behavior is very common in persons with substance use disorders. Drug-seeking tactics include emergency calls or visits near the end of office hours, refusal to undergo appropriate examination, testing, or referral, repeated “loss” of prescriptions, tampering with prescriptions, and reluctance to provide prior medical records or contact information for other treating healthcare provider(s). "Doctor shopping" (visiting multiple prescribers to obtain additional prescriptions) is common among people who abuse drugs and people with substance use disorder. Pre-occupation with achieving adequate pain relief can be appropriate behavior in a patient with inadequate pain control.

Oxymorphone Hydrochloride Extended-Release Tablets, like other opioids, can be diverted for non-medical use into illicit channels of distribution. Careful record-keeping of prescribing information, including quantity, frequency, and renewal requests, as required by state and federal law, is strongly advised.

Proper assessment of the patient, proper prescribing practices, periodic reevaluation of therapy, and proper dispensing and storage are appropriate measures that help to limit abuse of opioid drugs.

Risks Specific to Abuse of Oxymorphone Hydrochloride Extended-Release Tablets

Abuse of Oxymorphone Hydrochloride Extended-Release Tablets poses a risk of overdose and death. This risk is increased with concurrent use of Oxymorphone Hydrochloride Extended-Release Tablets with alcohol and/or other CNS depressants. Taking cut, broken, chewed, crushed, or dissolved Oxymorphone Hydrochloride Extended-Release Tablets enhance drug release and increases the risk of overdose and death [see Warnings and Precautions (5.1, 5.3) and Drug Interactions (7)].

Oxymorphone Hydrochloride Extended-Release Tablets are approved for oral use only. Parenteral drug abuse is commonly associated with transmission of infectious diseases such as hepatitis and HIV.

9.3 Dependence

Both tolerance and physical dependence can develop during use of opioid therapy. Tolerance is a physiological state characterized by a reduced response to a drug after repeated administration (i.e., a higher dose of a drug is required to produce the same effect that was once obtained at a lower dose).

Physical dependence is a state that develops as a result of a physiological adaptation in response to repeated drug use, manifested by withdrawal signs and symptoms after abrupt discontinuation or a significant dose reduction of a drug.

Withdrawal may be precipitated through the administration of drugs with opioid antagonist activity (e.g., naloxone, nalmefene), mixed agonist/antagonist analgesics (e.g., pentazocine, butorphanol, nalbuphine), or partial agonists (e.g., buprenorphine). Physical dependence may not occur to a clinically significant degree until after several days to weeks of continued use.

Do not rapidly reduce or abruptly discontinue Oxymorphone Hydrochloride Extended-Release Tablets in a patient physically dependent on opioids. Rapid reduction or abrupt discontinuation of Oxymorphone Hydrochloride Extended-Release Tablets in a patient physically dependent on opioids may lead to serious withdrawal symptoms, uncontrolled pain, and suicide. Rapid reduction or abrupt discontinuation has also been associated with attempts to find other sources of opioid analgesics, which may be confused with drug-seeking for abuse.

When discontinuing Oxymorphone Hydrochloride Extended-Release Tablets, gradually taper the dosage using a patient-specific plan that considers the following: the dose of Oxymorphone Hydrochloride Extended-Release Tablets the patient has been taking, the duration of treatment, and the physical and psychological attributes of the patient. To improve the likelihood of a successful taper and minimize withdrawal symptoms, it is important that the opioid tapering schedule is agreed upon by the patient. In patients taking opioids for an extended period of time at high doses, ensure that a multimodal approach to pain management, including mental health support (if needed), is in place prior to initiating an opioid analgesic taper [see Dosage and Administration (2.5) and Warnings and Precautions (5.15)].

Infants born to mothers physically dependent on opioids will also be physically dependent and may exhibit respiratory difficulties and withdrawal signs [see Use in Specific Populations (8.1)].

10 OVERDOSAGE

Clinical Presentation

Acute overdosage with oxymorphone can be manifested by respiratory depression, somnolence progressing to stupor or coma, skeletal muscle flaccidity, cold and clammy skin, constricted pupils, and in some cases, pulmonary edema, bradycardia, hypotension, hypoglycemia, partial or completed airway obstruction, atypical snoring, and death. Marked mydriasis rather than miosis may be seen with severe hypoxia in overdose situations [see Clinical Pharmacology (12.2)]. Toxic leukoencephalopathy has been reported after opioid overdose and can present hours, days, or weeks after apparent recovery from the initial intoxication.

Treatment of Overdose

In case of overdose, priorities are the reestablishment of a patent and protected airway and institution of assisted or controlled ventilation, if needed. Employ other supportive measures (including oxygen, vasopressors) in the management of circulatory shock and pulmonary edema as indicated. Cardiac arrest or arrhythmias will require advanced life support measures.

For clinically significant respiratory or circulatory depression secondary to oxymorphone overdose, administer an opioid overdose reversal agent such as naloxone or nalmefene.

Because the duration of opioid reversal is expected to be less than the duration of action of oxymorphone in Oxymorphone Hydrochloride Extended-Release Tablets, carefully monitor the patient until spontaneous respiration is reliably re-established. Oxymorphone Hydrochloride Extended-Release Tablets will continue to release oxymorphone and add to the oxymorphone load for 24 to 48 hours or longer following ingestion, necessitating prolonged monitoring. If the response to an opioid overdose reversal agent is suboptimal or only brief in nature, administer additional reversal agent as directed by product’s prescribing information.

In an individual physically dependent on opioids, administration of the recommended usual dosage of the opioid overdose reversal agent will precipitate an acute withdrawal syndrome. The severity of the withdrawal symptoms experienced will depend on the degree of physical dependence and the dose of the reversal agent administered. If a decision is made to treat serious respiratory depression in the physically dependent patient, administration of the reversal agent should be initiated with care and by titration with smaller than usual doses of the reversal agent.

11 DESCRIPTION

Oxymorphone Hydrochloride Extended-Release Tablets, USP are for oral use and contain oxymorphone, an opioid agonist. Oxymorphone Hydrochloride Extended-Release Tablets, USP are supplied in 5 mg, 7.5 mg, 10 mg, 15 mg, 20 mg, 30 mg and 40 mg tablet strengths for oral administration. The tablet strength describes the amount of oxymorphone hydrochloride per tablet.

The tablets contain the following inactive ingredients: microcrystalline cellulose, lactose monohydrate, hypromellose, xanthan gum, magnesium stearate, polyvinyl alcohol - partially hydrolyzed, polyethylene glycol, talc, and titanium dioxide. The 5 mg, 7.5 mg, 10 mg, 20 mg and 40 mg tablets contain FD&C Yellow No. 6 Aluminum Lake. In addition, the 5 mg tablets contain FD&C Blue No. 2 and D&C Red No. 27. The 7.5 mg tablets contain FD&C Blue No. 2 and FD&C Red No. 40. The 10 mg tablets contain FD&C Red No. 40. The 20 mg tablets contain D&C Yellow No. 10 Aluminum Lake, FD&C Blue No. 1, and FD&C Blue No. 2. The 30 mg tablets contain Iron Oxide Yellow and Iron Oxide Black. The 40 mg tablets contain D&C Yellow No. 10 Aluminum Lake.

The chemical name of oxymorphone hydrochloride is 4,5α-epoxy-3, 14-dihydroxy-17-methylmorphinan-6-one hydrochloride. Oxymorphone hydrochloride, USP is a white or slightly off-white, odorless powder, which is sparingly soluble in alcohol and ether, but freely soluble in water. The molecular weight of oxymorphone hydrochloride is 337.80. The pKa1 and pKa2 of oxymorphone at 37°C are 8.17 and 9.54, respectively. The octanol/aqueous partition coefficient at 37°C and pH 7.4 is 0.98.

The structural formula for oxymorphone hydrochloride is as follows:

FDA approved dissolution test specifications differ from USP.

12 CLINICAL PHARMACOLOGY

12.1 Mechanism of Action

Oxymorphone is a full opioid agonist and is relatively selective for the mu-opioid receptor, although it can bind to other opioid receptors at higher doses. The principal therapeutic action of oxymorphone is analgesia. Like all full opioid agonists, there is no ceiling effect for analgesia with oxymorphone. Clinically, dosage is titrated to provide adequate analgesia and may be limited by adverse reactions, including respiratory and CNS depression.

The precise mechanism of the analgesic action is unknown. However, specific CNS opioid receptors for endogenous compounds with opioid-like activity have been identified throughout the brain and spinal cord and are thought to play a role in the analgesic effects of this drug.

12.2 Pharmacodynamics

CNS Depressant/Alcohol Interaction

Additive pharmacodynamic effects may be expected when Oxymorphone Hydrochloride Extended-Release Tablets are used in conjunction with alcohol, other opioids, or illicit drugs that cause central nervous system depression.

Effects on the Central Nervous System

Oxymorphone produces respiratory depression by direct action on brain stem respiratory centers. The respiratory depression involves a reduction in the responsiveness of the brain stem respiratory centers to both increases in carbon dioxide tension and electrical stimulation.

Oxymorphone causes miosis, even in total darkness. Pinpoint pupils are a sign of opioid overdose but are not pathognomonic (e.g., pontine lesions of hemorrhagic or ischemic origin may produce similar findings). Marked mydriasis rather than miosis may be seen with hypoxia in overdose situations.

Effects on the Gastrointestinal Tract and on Other Smooth Muscle

Oxymorphone causes a reduction in motility associated with an increase in smooth muscle tone in the antrum of the stomach and duodenum. Digestion of food in the small intestine is delayed and propulsive contractions are decreased. Propulsive peristaltic waves in the colon are decreased, while tone is increased to the point of spasm, resulting in constipation. Other opioid-induced effects may include a reduction in biliary and pancreatic secretions, spasm of sphincter of Oddi, transient elevations in serum amylase, and opioid-induced esophageal dysfunction (OIED).

Effects on the Cardiovascular System

Oxymorphone produces peripheral vasodilation which may result in orthostatic hypotension or syncope. Release of histamine can occur and may contribute to opioid-induced hypotension. Manifestations of histamine release and/ or peripheral vasodilation may include pruritis, flushing, red eyes, sweating, and/or orthostatic hypotension.

Effects on the Endocrine System

Opioids inhibit the secretion of adrenocorticotropic hormone (ACTH), cortisol, and luteinizing hormone (LH) in humans [see Adverse Reactions (6.2)]. They also stimulate prolactin, growth hormone (GH) secretion, and pancreatic secretion of insulin and glucagon.

Use of opioids for an extended period of time may influence the hypothalamic-pituitary-gonadal axis, leading to androgen deficiency that may manifest as low libido, impotence, erectile dysfunction, amenorrhea, or infertility. The causal role of opioids in the clinical syndrome of hypogonadism is unknown because the various medical, physical, lifestyle, and psychological stressors that may influence gonadal hormone levels have not been adequately controlled for in studies conducted to date [see Adverse Reactions (6.2)].

Effects on the Immune System

Opioids have been shown to have a variety of effects on components of the immune system in in vitro and animal models. The clinical significance of these findings is unknown. Overall, the effects of opioids appear to be modestly immunosuppressive.

Concentration-Efficacy Relationships

The minimum effective analgesic concentration will vary widely among patients, especially among patients who have been previously treated with opioid agonists. The minimum effective analgesic concentration of oxymorphone for any individual patient may increase over time due to an increase in pain, development of a new pain syndrome and/or development of analgesic tolerance [see Dosage and Administration (2.1, 2.4)].

Concentration-Adverse Reaction Relationships

There is a relationship between increasing oxymorphone plasma concentration and increasing frequency of dose-related opioid adverse reactions such as nausea, vomiting, CNS effects, and respiratory depression. In opioid-tolerant patients, the situation may be altered by the development of tolerance to opioid-related adverse reactions [see Dosage and Administration (2.1, 2.3, 2.4)].

12.3 Pharmacokinetics

Absorption

The absolute oral bioavailability of oxymorphone is approximately 10%.

Steady-state levels are achieved after three days of multiple dose administration. Under both single-dose and steady-state conditions, dose proportionality has been established for the 5 mg, 10 mg, 20 mg, and 40 mg doses of Oxymorphone Hydrochloride Extended-Release Tablets, for both peak plasma levels (Cmax) and extent of absorption (AUC) (see Table 6).

Table 6: Mean (±SD) Oxymorphone Hydrochloride Extended-Release Tablets Pharmacokinetic Parameters

Regimen | Dosage | Cmax; (ng/mL) | AUC; (ng∙hr/mL) | T1/2; (hr)
Single Dose | 5 mg | 0.27±0.13 | 4.54±2.04 | 11.30±10.81
 | 10 mg | 0.65±0.29 | 8.94±4.16 | 9.83±5.68
 | 20 mg | 1.21±0.77 | 17.81±7.22 | 9.89±3.21
 | 40 mg | 2.59±1.65 | 37.90±16.20 | 9.35±2.94
Multiple Dose* | 5 mg | 0.70±0.55 | 5.60±3.87 | NA
 | 10 mg | 1.24±0.56 | 9.77±3.52 | NA
 | 20 mg | 2.54±1.35 | 19.28±8.32 | NA
 | 40 mg | 4.47±1.91 | 36.98±13.53 | NA
NA = not applicable
* Results after 5 days of q12h dosing.

Food Effect

Two studies examined the effect of food on the bioavailability of single doses of 20 mg and 40 mg of Oxymorphone Hydrochloride Extended-Release Tablets in healthy volunteers. In both studies, after the administration of Oxymorphone Hydrochloride Extended-Release Tablets, the Cmax was increased by approximately 50% in fed subjects compared to fasted subjects. A similar increase in Cmax was also observed with oxymorphone solution.

The AUC was unchanged in one study and increased by approximately 18% in the other study in fed subjects following the administration of Oxymorphone Hydrochloride Extended-Release Tablets. Examination of the AUC suggests that most of the difference between fed and fasting conditions occurs in the first four hours after dose administration. After oral dosing with a single dose of 40 mg, a peak oxymorphone plasma level of 2.8 ng/ml is achieved at 1 hour in fasted subjects and a peak of 4.25 ng/ml is achieved at 2 hours in fed subjects and that beyond the 12-hour time point, there is very little difference in the curves. As a result, Oxymorphone Hydrochloride Extended-Release Tablets should be dosed at least one hour prior to or two hours after eating [see Dosage and Administration (2.1, 2.3)].

Distribution

Formal studies on the distribution of oxymorphone in various tissues have not been conducted. Oxymorphone is not extensively bound to human plasma proteins; binding is in the range of 10% to 12%.

Elimination

Metabolism

Oxymorphone is highly metabolized, principally in the liver, and undergoes reduction or conjugation with glucuronic acid to form both active and inactive metabolites. The two major metabolites of oxymorphone are oxymorphone-3-glucuronide and 6-OH-oxymorphone. The mean plasma AUC for oxymorphone-3-glucuronide is approximately 90-fold higher than the parent compound. The pharmacologic activity of the glucuronide metabolite has not been evaluated. 6-OH-oxymorphone has been shown in animal studies to have analgesic bioactivity. The mean plasma 6-OH-oxymorphone AUC is approximately 70% of the oxymorphone AUC following single oral doses but is essentially equivalent to the parent compound at steady-state.

Excretion

Because oxymorphone is extensively metabolized, <1% of the administered dose is excreted unchanged in the urine. On average, 33% to 38% of the administered dose is excreted in the urine as oxymorphone-3-glucuronide and less than 1% excreted as 6-OH-oxymorphone in subjects with normal hepatic and renal function. In animals given radiolabeled oxymorphone, approximately 90% of the administered radioactivity was recovered within 5 days of dosing. The majority of oxymorphone-derived radioactivity was found in the urine and feces.

Specific Populations

Geriatric Patients

The steady-state plasma concentrations of oxymorphone, 6-OH-oxymorphone, and oxymorphone-3-glucuronide are approximately 40% higher in elderly subjects (≥65 years of age) than in young subjects (18 to 40 years of age). On average, age greater than 65 years was associated with a 1.4-fold increase in oxymorphone AUC and a 1.5-fold increase in Cmax. This observation does not appear related to a difference in body weight, metabolism, or excretion of oxymorphone [see Use in Specific Populations (8.5)].

Sex

The effect of sex was evaluated following single- and multiple-doses of Oxymorphone Hydrochloride Extended-Release Tablets in male and female adult volunteers. There was a consistent tendency for female subjects to have slightly higher AUCss and Cmax values than male subjects; however, sex differences were not observed when AUCss and Cmax were adjusted by body weight.

Hepatic Impairment

The bioavailability of orally administered oxymorphone is markedly increased in patients with moderate to severe liver disease. The disposition of oxymorphone was compared in six patients with mild, five patients with moderate, and one patient with severe hepatic impairment and 12 subjects with normal hepatic function. The bioavailability of oxymorphone was increased by 1.6-fold in patients with mild hepatic impairment and by 3.7-fold in patients with moderate hepatic impairment. In one patient with severe hepatic impairment, the bioavailability was increased by 12.2-fold. The half-life of oxymorphone was not significantly affected by hepatic impairment.

Renal Impairment

Data from a pharmacokinetic study involving 24 patients with renal dysfunction show an increase of 26%, 57%, and 65% in oxymorphone bioavailability in mild (creatinine clearance 51 mL/min to 80 mL/min; n=8), moderate (creatinine clearance 30 mL/min to 50 mL/min; n=8), and severe (creatinine clearance < 30 mL/min; n=8) patients, respectively, compared to healthy controls.

Drug Interaction Studies

Alcohol Interaction

An in vivo study of the effect of alcohol (40%, 20%, 4% and 0%) on the bioavailability of a single dose of 40 mg of Oxymorphone Hydrochloride Extended-Release Tablets in healthy, fasted volunteers demonstrated a highly variable effect on Cmax with concomitant administration of alcohol and Oxymorphone Hydrochloride Extended-Release Tablets. The change in Cmax ranged from a decrease of 50% to an increase of 270% across all conditions studied. Following administration of 240 mL of 40% ethanol, the Cmax increased on average by 70% and up to 270% in individual subjects. Following the concomitant administration of 240 mL of 20% ethanol, the Cmax increased on average by 31% and up to 260% in individual subjects. Following the concomitant administration of 240 mL of 4% ethanol, the Cmax increased 7% on average and by as much as 110% for individual subjects. After oral dosing with a single dose of 40 mg in fasted subjects, the mean peak oxymorphone plasma level is 2.4 ng/mL and the median Tmax is 2 hours. Following co-administration of Oxymorphone Hydrochloride Extended-Release Tablets and alcohol (240 mL of 40% ethanol) in fasted subjects, the mean peak oxymorphone level is 3.9 ng/mL and the median Tmax is 1.5 hours (range 0.75 to 6 hours). The oxymorphone mean AUC was 13% higher after co-administration of 240 mL of 40% alcohol. The AUC was essentially unaffected in subjects following the co-administration of Oxymorphone Hydrochloride Extended-Release Tablets and ethanol (240 mL of 20% or 4% ethanol).

In vitro studies have demonstrated that Oxymorphone Hydrochloride Extended-Release Tablets do not release oxymorphone more rapidly in 500 mL of 0.1N Hydrochloride solutions containing ethanol (4%, 20% and 40%).

Instruct patients to avoid use of alcohol when taking Oxymorphone Hydrochloride Extended-Release Tablets.

In vitro studies revealed little to no biotransformation of oxymorphone to 6-OH-oxymorphone by any of the major cytochrome P450 (CYP P450) isoforms at therapeutically relevant oxymorphone plasma concentrations.

No inhibition of any of the major CYP P450 isoforms was observed when oxymorphone was incubated with human liver microsomes at concentrations of ≤15.1 mcg/mL. An inhibition of CYP3A4 activity occurred at oxymorphone concentrations ≥45.3 mcg/mL. Therefore, it is not expected that oxymorphone, or its metabolites will act as inhibitors of any of the major CYP P450 enzymes in vivo.

Increases in the activity of the CYP 2C9 and CYP 3A4 isoforms occurred when oxymorphone was incubated with human hepatocytes. However, clinical drug interaction studies with Oxymorphone Hydrochloride Extended-Release Tablets showed no induction of CYP450 3A4 or 2C9 enzyme activity, indicating that no dose adjustment for CYP 3A4- or 2C9-mediated drug-drug interactions is required.

13 NONCLINICAL TOXICOLOGY

13.1 Carcinogenesis, Mutagenesis, Impairment of Fertility

Carcinogenesis

No evidence of carcinogenic potential was observed in long-term animal studies in mice and rats. Oxymorphone hydrochloride was administered to Sprague Dawley rats (2.5 mg/kg/day, 5 mg/kg/day and 10 mg/kg/day in males and 5 mg/kg/day, 10 mg/kg/day and 25 mg/kg/day in females) for 2 years by oral gavage. Systemic drug exposure (AUC) at the highest doses tested in male and female rats was 4.8 times and 21.2 times the human exposure at a dose of 20 mg/day, respectively. Oxymorphone hydrochloride was administered to male and female CD-1 mice (10 mg/kg/day, 25 mg/kg/day, 75 mg/kg/day and 150 mg/kg/day) for 2 years by oral gavage. Systemic drug exposure (AUC) at 150 mg/kg/day in male and female mice was 205 times and 243 times the human exposure at a dose of 20 mg/day, respectively.

Mutagenesis

Oxymorphone hydrochloride was not mutagenic when tested in the in vitro bacterial reverse mutation assay (Ames test), or in an in vitro mammalian cell chromosome aberration assay performed with human peripheral blood lymphocytes. Oxymorphone hydrochloride tested positive in both the rat and mouse in vivo micronucleus assays. An increase in micronucleated polychromatic erythrocytes occurred in mice given doses ≥ 250 mg/kg and in rats given doses of 20 mg/kg and 40 mg/kg. A subsequent study demonstrated that oxymorphone hydrochloride was not aneugenic in mice following administration of up to 500 mg/kg. Additional studies indicate that the increased incidence of micronucleated polychromatic erythrocytes in rats may be secondary to increased body temperature following oxymorphone administration. Doses associated with increased micronucleated polychromatic erythrocytes also produce a marked, rapid increase in body temperature. Pretreatment of animals with sodium salicylate minimized the increase in body temperature and prevented the increase in micronucleated polychromatic erythrocytes after administration of 40 mg/kg oxymorphone.

Impairment of Fertility

Female rats were treated with oxymorphone hydrochloride beginning 14 days prior to mating through Gestation Day 7 via oral gavage doses of 5 mg/kg/day, 10 mg/kg/day or 25 mg/kg/day (2.4, 4.9, or 12.2 times the human daily dose of 20 mg/day based on body surface area, respectively). Male rats were treated via oral gavage with the same oxymorphone hydrochloride doses beginning 28 days prior to and throughout mating. In female rats, an increase in the length of the estrus cycle and decrease in the mean number of viable embryos, implantation sites and corpora lutea were observed at 4.9 times the human dose of 20 mg/day. No adverse effects of oxymorphone on male reproductive function or sperm parameters were observed.

14 CLINICAL STUDIES

The efficacy and safety of Oxymorphone Hydrochloride Extended-Release Tablets have been evaluated in double-blind, controlled clinical trials in patients who were not opioid tolerant and opioid-experienced patients with moderate to severe pain including low back pain.

12-Week Study in Patients who were not Opioid Tolerant with Low Back Pain

Patients with chronic low back pain who were suboptimally responsive to their non-opioid therapy entered a 4-week, open-label dose titration phase. Patients initiated therapy with two days of treatment with Oxymorphone Hydrochloride Extended-Release Tablets 5 mg, every 12 hours. Thereafter, patients were titrated to a stabilized dose, at increments of 5 mg to 10 mg every 12 hours every 3 to 7 days. Of the patients who were able to stabilize within the Open-Label Titration Period, the mean±SD VAS score at Screening was 69.4±11.8 mm and at Baseline (beginning of Double-Blind Period) were 18.5±11.2 mm and 19.3±11.3 mm for the oxymorphone ER and placebo groups, respectively. Sixty-three percent of the patients enrolled were able to titrate to a tolerable dose and were randomized into a 12-week double-blind treatment phase with placebo or their stabilized dose of Oxymorphone Hydrochloride Extended-Release Tablets. The mean±SD stabilized doses were 39.2±26.4 mg and 40.9±25.3 mg for the Oxymorphone Hydrochloride Extended-Release Tablets and placebo groups, respectively; total daily doses ranged from 10 mg to 140 mg. During the first 4 days of double-blind treatment patients were allowed an unlimited number of oxymorphone hydrochloride tablets, an immediate-release (IR) formulation of oxymorphone, 5 mg tablets, every 4 to 6 hours as supplemental analgesia; thereafter the number of oxymorphone hydrochloride tablets was limited to two tablets per day. This served as a tapering method to minimize opioid withdrawal symptoms in placebo patients. Sixty-eight percent of patients treated with Oxymorphone Hydrochloride Extended-Release Tablets completed the 12-week treatment compared to 47% of patients treated with placebo. Oxymorphone Hydrochloride Extended-Release Tablets provided superior analgesia compared to placebo. The analgesic effect of Oxymorphone Hydrochloride Extended-Release Tablets was maintained throughout the double-blind treatment period in 89% of patients who completed the study. These patients reported a decrease, no change, or a ≤ 10 mm increase in VAS score from Day 7 until the end of the study.

The proportion of patients with various degrees of improvement from screening to study endpoint is shown in Figure 1. The figure is cumulative, so that patients whose change from baseline is, for example, 30%, are also included at every level of improvement below 30%. Patients who did not complete the study were assigned 0% improvement.

Figure 1: Percent Reduction in Average Pain Intensity from Screening to Final Visit

12-Week Study in Opioid-Experienced Patients with Low Back Pain

Patients on chronic opioid therapy entered a 4-week, open-label titration phase with Oxymorphone Hydrochloride Extended-Release Tablets dosed every 12 hours at an approximated equianalgesic dose of their pre-study opioid medication. Of the patients who were able to stabilize within the Open‑Label Titration Period, the mean±SD VAS score at Screening was 69.5±17.0 mm and at Baseline (beginning of Double-Blind Period) were 23.9±12.1 mm and 22.2±10.8 mm for the oxymorphone ER and placebo groups, respectively. Stabilized patients entered a 12‑week double-blind treatment phase with placebo or their stabilized dose of Oxymorphone Hydrochloride Extended-Release Tablets. The mean±SD stabilized doses were 80.9±59.3 mg and 93.3±61.3 mg for the Oxymorphone Hydrochloride Extended-Release Tablets and placebo groups, respectively; total daily doses ranged from 20 mg to 260 mg. During the first 4 days of double-blind treatment, patients were allowed an unlimited number of oxymorphone hydrochloride 5 mg tablets, every 4 to 6 hours as supplemental analgesia; thereafter the number of oxymorphone hydrochloride tablets was limited to two tablets per day. This served as a tapering method to minimize opioid withdrawal symptoms in placebo patients. Fifty-seven percent of patients were titrated to a stabilized dose within approximately 4 weeks of Oxymorphone Hydrochloride Extended-Release Tablets dose titration. Seventy percent of patients treated with Oxymorphone Hydrochloride Extended-Release Tablets and 26% of patients treated with placebo completed the 12-week treatment. Oxymorphone Hydrochloride Extended-Release Tablets provided superior analgesia compared to placebo. The analgesic effect of Oxymorphone Hydrochloride Extended-Release Tablets was maintained throughout the double-blind treatment period in 80% of patients who completed the study. These patients reported a decrease, no change, or a ≤ 10 mm increase in VAS score from Day 7 until the end of the study.

The proportion of patients with various degrees of improvement from screening to study endpoint is shown in Figure 2. The figure is cumulative, so that patients whose change from baseline is, for example, 30%, are also included at every level of improvement below 30%. Patients who did not complete the study were assigned 0% improvement.

Figure 2: Percent Reduction in Average Pain Intensity from Screening to Final Visit

16 HOW SUPPLIED/STORAGE AND HANDLING

Oxymorphone Hydrochloride Extended-Release Tablets, USP are supplied as the following strengths:

Oxymorphone Hydrochloride Extended-Release Tablets USP, 5 mg are purple, round, film-coated extended-release tablets debossed with “G71” on one side and blank on the other side.

They are available as follows:

Bottles of 30: NDC 64896-695-08

Bottles of 60: NDC 64896-695-13

Bottles of 100: NDC 64896-695-01

Bottles of 1000: NDC 64896-695-03

Oxymorphone Hydrochloride Extended-Release Tablets USP, 7.5 mg are gray, round, film-coated extended-release tablets debossed with “G75” on one side and blank on the other side.

They are available as follows:

Bottles of 30: NDC 64896-696-08

Bottles of 60: NDC 64896-696-13

Bottles of 100: NDC 64896-696-01

Bottles of 1000: NDC 64896-696-03

Oxymorphone Hydrochloride Extended-Release Tablets USP, 10 mg are orange, round, film-coated extended-release tablets debossed with “G72” on one side and blank on the other side.

They are available as follows:

Bottles of 30: NDC 64896-697-08

Bottles of 60: NDC 64896-697-13

Bottles of 100: NDC 64896-697-01

Bottles of 1000: NDC 64896-697-03

Oxymorphone Hydrochloride Extended-Release Tablets USP, 15 mg are white, round, film-coated extended-release tablets debossed with “G76” on one side and blank on the other side.

They are available as follows:

Bottles of 30: NDC 64896-698-08

Bottles of 60: NDC 64896-698-13

Bottles of 100: NDC 64896-698-01

Bottles of 1000: NDC 64896-698-03

Oxymorphone Hydrochloride Extended-Release Tablets USP, 20 mg are green, round, film-coated extended-release tablets debossed with “G73” on one side and blank on the other side.

They are available as follows:

Bottles of 30: NDC 64896-699-08

Bottles of 60: NDC 64896-699-13

Bottles of 100: NDC 64896-699-01

Bottles of 1000: NDC 64896-699-03

Oxymorphone Hydrochloride Extended-Release Tablets USP, 30 mg are brown, round, film-coated extended-release tablets debossed with “G77” on one side and blank on the other side.

They are available as follows:

Bottles of 30: NDC 64896-700-08

Bottles of 60: NDC 64896-700-13

Bottles of 100: NDC 64896-700-01

Bottles of 1000: NDC 64896-700-03

Oxymorphone Hydrochloride Extended-Release Tablets USP, 40 mg are orange, round, film-coated extended-release tablets debossed with “G74” on one side and blank on the other side.

They are available as follows:

Bottles of 30: NDC 64896-701-08

Bottles of 60: NDC 64896-701-13

Bottles of 100: NDC 64896-701-01

Bottles of 1000: NDC 64896-701-03

Store at 20° to 25°C (68° to 77°F) [see USP Controlled Room Temperature].

Dispense in tight container as defined in the USP, with a child-resistant closure (as required).

Store Oxymorphone Hydrochloride Extended-Release Tablets securely and dispose of properly.

17 PATIENT COUNSELING INFORMATION

Advise the patient to read the FDA-approved patient labeling (Medication Guide).

Storage and Disposal

Because of the risks associated with accidental ingestion, misuse, and abuse, advise patients to store Oxymorphone Hydrochloride Extended-Release Tablets securely, out of sight and reach of children, and in a location not accessible by others, including visitors to the home. Inform patients that leaving Oxymorphone Hydrochloride Extended-Release Tablets unsecured can pose a deadly risk to others in the home [see Warnings and Precautions (5.1, 5.2) and Drug Abuse and Dependence (9.2)].

Advise patients and caregivers that when medicines are no longer needed, they should be disposed of promptly. Expired, unwanted, or unused Oxymorphone Hydrochloride Extended-Release Tablets should be disposed of by flushing the unused medication down the toilet if a drug take-back option is not readily available. Inform patients that they can visit www.fda.gov/drugdisposal for a complete list of medicines recommended for disposal by flushing, as well as additional information on disposal of unused medicines.

Addiction, Abuse, and Misuse

Inform patients that the use of Oxymorphone Hydrochloride Extended-Release Tablets, even when taken as recommended, can result in addiction, abuse, and misuse, which can lead to overdose or death [see Warnings and Precautions (5.1)]. Instruct patients not to share Oxymorphone Hydrochloride Extended-Release Tablets with others and to take steps to protect Oxymorphone Hydrochloride Extended-Release Tablets from theft or misuse.

Life-Threatening Respiratory Depression

Inform patients of the risk of life-threatening respiratory depression, including information that the risk is greatest when starting Oxymorphone Hydrochloride Extended-Release Tablets or when the dosage is increased, and that it can occur even at recommended doses.

Educate patients and caregivers on how to recognize respiratory depression and emphasize the importance of calling 911 or getting emergency medical help right away in the event of a known or suspected overdose [see Warnings and Precautions (5.2)].

Accidental Ingestion

Inform patients that accidental ingestion, especially by children, may result in respiratory depression or death [see Warnings and Precautions (5.2)].

Interactions with Benzodiazepines and other CNS Depressants

Instruct patients not to consume alcoholic beverages, as well as prescription and over-the-counter products that contain alcohol, during treatment with Oxymorphone Hydrochloride Extended-Release Tablets. The co-ingestion of alcohol with Oxymorphone Hydrochloride Extended-Release Tablets may result in increased plasma levels and a potentially fatal overdose of oxymorphone [see Warnings and Precautions (5.3) and Drug Interactions (7)].

Inform patients and caregivers that potentially fatal additive effects may occur if Oxymorphone Hydrochloride Extended-Release Tablets are used with benzodiazepines or other CNS depressants, including alcohol (e.g., non-benzodiazepine sedative/hypnotics, anxiolytics, tranquilizers, muscle relaxants, general anesthetics, antipsychotics, gabapentinoids [gabapentin or pregabalin], and other opioids)l, and not to use these concomitantly unless supervised by a health care provider [see Warnings and Precautions (5.3) and Drug Interactions (7)].

Patient Access to an Opioid Overdose Reversal Agent for the Emergency Treatment of Opioid Overdose

Inform patients and caregivers about opioid overdose reversal agents (e.g., naloxone, nalmefene). Discuss the importance of having access to an opioid overdose reversal agent, especially if the patient has risk factors for overdose (e.g., concomitant use of CNS depressants, a history of opioid use disorder, or prior opioid overdose) or if there are household members (including children) or other close contacts at risk for accidental ingestion

or opioid overdose.

Discuss with the patient the options for obtaining an opioid overdose reversal agent (e.g., prescription, over-the-counter, or as part of a community-based program) [see Dosage and Administration (2.2), Warnings and Precautions (5.3)].

Educate patients and caregivers on how to recognize the signs and symptoms of an overdose.

Explain to patients and caregivers that effects of opioid overdose reversal agents like naloxone and nalmefene are temporary, and that they must call 911 or get emergency medical help right away in all cases of known or suspected opioid overdose, even if an opioid overdose reversal agent is administered [see Overdosage (10)].

Advise patients and caregivers:

- how to treat with the overdose reversal agent in the event of an opioid overdose.
- to tell family and friends about their opioid overdose reversal agent, and to keep it in a place where family and friends can access it in an emergency.
- to read the Patient Information (or other educational material) that will come with their opioid overdose reversal agent. Emphasize the importance of doing this before an opioid emergency happens, so the patient and caregiver will know what to do.

Hyperalgesia and Allodynia

Inform patients and caregivers not to increase opioid dosage without first consulting a clinician. Advise patients to seek medical attention if they experience symptoms of hyperalgesia, including worsening pain, increased sensitivity to pain, or new pain [see Warnings and Precautions (5.6) and Adverse Reactions (6.2)].

Anaphylaxis, Angioedema, and Other Hypersensitivity Reactions

Inform patients that anaphylaxis and other hypersensitivity reactions have been reported with ingredients contained in Oxymorphone Hydrochloride Extended-Release Tablets. Advise patients how to recognize such a reaction and when to seek medical attention [see Contraindications (4), Warnings and Precautions (5.8) and Adverse Reactions (6)].

Serotonin Syndrome

Inform patients that opioids could cause a rare but potentially life-threatening condition called serotonin syndrome resulting from concomitant administration of serotonergic drugs. Warn patients of the symptoms of serotonin syndrome and to seek medical attention right away if symptoms develop. Instruct patients to inform their physicians if they are taking, or plan to take serotonergic medications [see Drug Interactions (7)].

MAOI Interaction

Inform patients to avoid taking Oxymorphone Hydrochloride Extended-Release Tablets while using any drugs that inhibit monoamine oxidase. Patients should not start MAOIs while taking Oxymorphone [see Drug Interactions (7)].

Important Administration Instructions

Instruct patients how to properly take Oxymorphone Hydrochloride Extended-Release Tablets, including the following:

- Oxymorphone Hydrochloride Extended-Release Tablets are designed to work properly only if swallowed intact. Taking cut, broken, chewed, crushed, or dissolved Oxymorphone Hydrochloride Extended-Release Tablets can result in a fatal overdose [see Dosage and Administration (2.1)].
- Use Oxymorphone Hydrochloride Extended-Release Tablets exactly as prescribed to reduce the risk of life-threatening adverse reactions (e.g., respiratory depression) [see Dosage and Administration (2) and Warnings and Precautions (5.2)].

Important Discontinuation Instructions

In order to avoid developing withdrawal symptoms, instruct patients not to discontinue Oxymorphone Hydrochloride Extended-Release Tablets without first discussing a tapering plan with the prescriber [see Dosage and Administration (2.5)].

Driving or Operating Heavy Machinery

Inform patients that Oxymorphone Hydrochloride Extended-Release Tablets may impair the ability to perform potentially hazardous activities such as driving a car or operating heavy machinery. Advise patients not to perform such tasks until they know how they will react to the medication [see Warnings and Precautions (5.16)].

Constipation

Advise patients of the potential for severe constipation, including management instructions and when to seek medical attention [see Adverse Reactions (6) and Clinical Pharmacology (12.2)].

Adrenal Insufficiency

Inform patients that Oxymorphone Hydrochloride Extended-Release Tablets could cause adrenal insufficiency, a potentially life-threatening condition. Adrenal insufficiency may present with non-specific symptoms and signs such as nausea, vomiting, anorexia, fatigue, weakness, dizziness, and low blood pressure. Advise patients to seek medical attention if they experience a constellation of these symptoms [see Warnings and Precautions (5.9)].

Hypotension

Inform patients that Oxymorphone Hydrochloride Extended-Release Tablets may cause orthostatic hypotension and syncope. Instruct patients how to recognize symptoms of low blood pressure and how to reduce the risk of serious consequences should hypotension occur (e.g., sit or lie down, carefully rise from a sitting or lying position).

Pregnancy

Neonatal Opioid Withdrawal Syndrome

Inform female patients of reproductive potential that use of Oxymorphone Hydrochloride Extended-Release Tablets for an extended period of time during pregnancy can result in neonatal opioid withdrawal syndrome, which may be life-threatening if not recognized and treated [see Warnings and Precautions (5.4) and Use in Specific Populations (8.1)].

Embryo-Fetal Toxicity

Inform female patients of reproductive potential that Oxymorphone Hydrochloride Extended-Release Tablets can cause fetal harm and to inform their healthcare provider of a known or suspected pregnancy [see Use in Specific Populations (8.1)].

Lactation

Advise patients that breastfeeding is not recommended during treatment with Oxymorphone Hydrochloride Extended-Release Tablets [see Use in Specific Populations (8.2)].

Infertility

Inform patients that use of opioids for an extended period of time may cause reduced fertility. It is not known whether these effects on fertility are reversible [see Adverse Reactions (6.2) and Use in Specific Populations (8.3)].

Manufactured by:
Amneal Pharmaceuticals of NY, LLC
Brookhaven, NY 11719

Distributed by:
Amneal Specialty, a division of Amneal Pharmaceuticals LLC
Bridgewater, NJ 08807

Rev. 01-2026-08

Medication Guide

Oxymorphone Hydrochloride (ox” i mor’ fone hy” droe klor’ ide) Extended-Release Tablets, USP for oral use, CII

Oxymorphone Hydrochloride Extended-Release Tablets are:

- A strong prescription pain medicine that contains an opioid (narcotic) that is used to manage severe and persistent pain that requires an extended treatment period with a daily opioid pain medicine, when other pain medicines do not treat your pain well enough or you cannot tolerate them.
- A long-acting (extended-release) opioid pain medicine that can put you at risk for overdose and death. Even if you take your dose correctly as prescribed you are at risk for opioid addiction, abuse, and misuse that can lead to death.
- Not to be taken on an “as needed” basis.

Important information about Oxymorphone Hydrochloride Extended-Release Tablets:

- Get emergency help or call 911 right away if you take too much Oxymorphone Hydrochloride Extended-Release Tablets (overdose). When you first start taking Oxymorphone Hydrochloride Extended-Release Tablets, when your dose is changed, or if you take too much (overdose), serious or life-threatening breathing problems that can lead to death may occur. Ask your healthcare provider about medicines like naloxone or nalmefene that can be used in an emergency to reverse an opioid overdose.
- Taking Oxymorphone Hydrochloride Extended-Release Tablets with other opioid medicines, benzodiazepines, gabapentinoids (gabapentin or pregabalin), alcohol, or other central nervous system depressants (including street drugs) can cause severe drowsiness, decreased awareness, breathing problems, coma, and death.
- Never give anyone else your Oxymorphone Hydrochloride Extended-Release Tablets. They could die from taking it. Selling or giving away Oxymorphone Hydrochloride Extended-Release Tablets is against the law.
- Store Oxymorphone Hydrochloride Extended-Release Tablets securely, out of sight and reach of children, and in a location not accessible by others, including visitors to the home.

Do not take Oxymorphone Hydrochloride Extended-Release Tablets if you have:

- severe asthma, trouble breathing, or other lung problems.
- a bowel blockage or have narrowing of the stomach or intestines.

Before taking Oxymorphone Hydrochloride Extended-Release Tablets, tell your healthcare provider if you have a history of:

- head injury, seizures
- problems urinating
- abuse of street or prescription drugs, alcohol addiction, opioid overdose, or mental health problems
- liver, kidney, thyroid problems
- pancreas or gallbladder problems

Tell your healthcare provider if you are:

- noticing your pain getting worse. If your pain gets worse after you take Oxymorphone Hydrochloride Extended-Release Tablets, do not take more of Oxymorphone Hydrochloride Extended-Release Tablets without first talking to your healthcare provider. Talk to your healthcare provider if the pain that you have increases, if you feel more sensitive to pain, or if you have new pain after taking Oxymorphone Hydrochloride Extended-Release Tablets.
- pregnant or planning to become pregnant. Use of Oxymorphone Hydrochloride Extended-Release Tablets for an extended period of time during pregnancy can cause withdrawal symptoms in your newborn baby that could be life-threatening if not recognized and treated.
- breastfeeding. Not recommended during treatment with Oxymorphone Hydrochloride Extended-Release Tablets. It may harm your baby.
- living in a household where there are small children or someone who has abused street or prescription drugs.
- taking prescription or over-the-counter medicines, vitamins, or herbal supplements. Taking Oxymorphone Hydrochloride Extended-Release Tablets with certain other medicines can cause serious side effects that could lead to death.

When taking Oxymorphone Hydrochloride Extended-Release Tablets:

- Do not change your dose. Take Oxymorphone Hydrochloride Extended-Release Tablets exactly as prescribed by your healthcare provider. Use the lowest dose possible for the shortest time needed.
- Take your prescribed dose every 12 hours at the same time every day on an empty stomach, at least 1 hour before or 2 hours after meals. Do not take more than your prescribed dose in 24 hours. If you miss a dose, take your next dose at your usual time.
- Swallow Oxymorphone Hydrochloride Extended-Release Tablets whole. Do not cut, break, chew, crush, dissolve, snort, or inject Oxymorphone Hydrochloride Extended-Release Tablets because this may cause you to overdose and die.
- Call your healthcare provider if the dose you are taking does not control your pain.
- Do not stop taking Oxymorphone Hydrochloride Extended-Release Tablets without talking to your healthcare provider.
- Dispose of expired, unwanted, or unused Oxymorphone Hydrochloride Extended-Release Tablets by promptly flushing down the toilet, if a drug take-back option is not readily available. Visit www.fda.gov/drugdisposal for additional information on disposal of unused medicines.

While taking Oxymorphone Hydrochloride Extended-Release Tablets DO NOT:

- Drive or operate heavy machinery, until you know how Oxymorphone Hydrochloride Extended-Release Tablets affect you. Oxymorphone Hydrochloride Extended-Release Tablets can make you sleepy, dizzy, or lightheaded.
- Drink alcohol or use prescription or over-the-counter medicines that contain alcohol. Using products containing alcohol during treatment with Oxymorphone Hydrochloride Extended-Release Tablets may cause you to overdose and die.

The possible side effects of Oxymorphone Hydrochloride Extended-Release Tablets:

- constipation, nausea, sleepiness, vomiting, tiredness, headache, dizziness, abdominal pain. Call your healthcare provider if you have any of these symptoms and they are severe.
  Get emergency medical help or call 911 right away if you have:
- trouble breathing, shortness of breath, fast heartbeat, chest pain, swelling of your face, tongue, or throat, or hands, hives, itching, rash, extreme drowsiness, light-headedness when changing positions, feeling faint, agitation, high body temperature, trouble walking, stiff muscles, or mental changes such as confusion.

These are not all the possible side effects of Oxymorphone Hydrochloride Extended-Release Tablets. Call your healthcare provider for medical advice about side effects. You may report side effects to FDA at 1-800-FDA-1088.

For more information go to dailymed.nlm.nih.gov.

For more information about Oxymorphone Hydrochloride Extended-Release Tablets, call Amneal Pharmaceuticals at 1-877-835-5472.

This Medication Guide has been approved by the U.S. Food and Drug Administration.

Manufactured by:
Amneal Pharmaceuticals of NY, LLC
Brookhaven, NY 11719

Distributed by:
Amneal Specialty, a division of Amneal Pharmaceuticals LLC
Bridgewater, NJ 08807

Rev. 10-2025-07